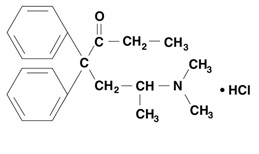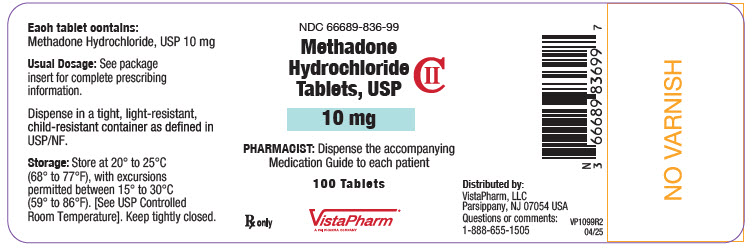 DRUG LABEL: Methadone Hydrochloride
NDC: 66689-836 | Form: TABLET
Manufacturer: VistaPharm, LLC
Category: prescription | Type: HUMAN PRESCRIPTION DRUG LABEL
Date: 20251231
DEA Schedule: CII

ACTIVE INGREDIENTS: METHADONE HYDROCHLORIDE 10 mg/1 1
INACTIVE INGREDIENTS: MAGNESIUM STEARATE; MICROCRYSTALLINE CELLULOSE; STARCH, CORN

HIGHLIGHTS OF PRESCRIBING INFORMATION

These highlights do not include all the information needed to use METHADONE HYDROCHLORIDE TABLETS safely and effectively. See full prescribing information for METHADONE HYDROCHLORIDE TABLETS.
METHADONE HYDROCHLORIDE tablets, for oral use CII
Initial U.S. Approval: 1947

WARNING: SERIOUS AND LIFE-THREATENING RISKS FROM USE OF METHADONE HYDROCHLORIDE TABLETS

See full prescribing information for complete boxed warning.

- Methadone hydrochloride tablets expose users to risks of addiction, abuse, and misuse, which can lead to overdose and death. Assess each patient’s risk before prescribing, and monitor regularly for development of these behaviors and conditions. (5.1)
- Serious, life-threatening, or fatal respiratory depression may occur. The peak respiratory depressant effect of methadone occurs later, and persists longer than the peak analgesic effect. Monitor closely, especially upon initiation or following a dose increase. (5.2)
- Accidental ingestion of methadone hydrochloride tablets, especially by children, can result in fatal overdose of methadone. (5.2)
- Concomitant use of opioids with benzodiazepines or other central nervous system (CNS) depressants, including alcohol, may result in profound sedation, respiratory depression, coma, and death. (5.3, 7)
- QT interval prolongation and serious arrhythmia (torsades de pointes) have occurred during treatment with methadone. Closely monitor patients with risk factors for development of prolonged QT interval, a history of cardiac conduction abnormalities, and those taking medications affecting cardiac conduction (5.4)
- Neonatal opioid withdrawal syndrome (NOWS) is an expected and treatable outcome of use of methadone hydrochloride tablets during pregnancy. NOWS may be life-threatening if not recognized and treated in the neonate. The balance between the risks of NOWS and the benefits of maternal methadone hydrochloride tablets use may differ based on the risks associated with the mother’s underlying condition, pain, or addiction. Advise the patient of the risk of NOWS so that appropriate planning for management of the neonate can occur. (5.5)
- To ensure that the benefits of opioid analgesics outweigh the risks of addiction, abuse, and misuse, the Food and Drug Administration (FDA) has required a Risk Evaluation and Mitigation Strategy (REMS) for these products. (5.6)
- Concomitant use with CYP3A4, 2B6, 2C19, 2C9 or 2D6 inhibitors or discontinuation of concomitantly used CYP3A4, 2B6, 2C19, or 2C9 inducers can result in a fatal overdose of methadone (5.7, 7)
- Methadone products, when used for the treatment of opioid addiction in detoxification or maintenance programs, shall be dispensed only by certified opioid treatment programs as stipulated in 42 CFR 8.12. (1, 2.1)

RECENT MAJOR CHANGES

Boxed Warning | 10/2025
Indications and Usage (1) | 10/2025
Dosage and Administration (2.3, 2.6) | 10/2025
Warnings and Precautions (5.1,5.2,5.3,5.14, 5.16) | 10/2025

1 INDICATIONS AND USAGE

1. Methadone hydrochloride tablet is indicated for the management of severe and persistent pain that requires an opioid analgesic and that cannot be adequately treated with alternative options, including immediate-release opioids.
  Limitations of Use
  - Because of the risks of addiction, abuse, misuse, overdose, and death, which can occur at any dosage or duration and persist over the course of therapy, reserve opioid analgesics, including methadone hydrochloride tablets, for use in patients for whom alternative treatment options are ineffective, not tolerated, or would be otherwise inadequate to provide sufficient management of pain (1, 5.1)
  - Methadone hydrochloride tablets are not indicated as an as-needed (prn) analgesic. (1)
2. Detoxification treatment of opioid addiction (heroin or other morphine-like drugs).
3. Maintenance treatment of opioid addiction (heroin or other morphine-like drugs), in conjunction with appropriate social and medical services. (1)
  Limitations of Use
  Methadone products used for the treatment of opioid addiction in detoxification or maintenance program are subject to the conditions for distribution and use required under 42 CFR 8.12. (2.1)

2 DOSAGE AND ADMINISTRATION

- Consider recommending or prescribing an opioid overdose reversal agent (e.g., naloxone, nalmefene) based on the patient’s risk factors for overdose (2.3, 5.1, 5.2, 5.3).
- Methadone hydrochloride tablets should be prescribed only by healthcare professionals who are knowledgeable about the use of extended-release/long-acting opioids and how to mitigate the associated risks. (2.1)
- Use the lowest effective dosage for the shortest duration of time consistent with individual patient treatment goals. Reserve titration to higher doses of methadone hydrochloride tablets for patients in whom lower doses are insufficiently effective and in whom the expected benefits of using a higher dose opioid clearly outweigh the substantial risks. (2.1,5)
- Initiate the dosing regimen for each patient individually, taking into account the patient’s underlying cause and severity of pain, prior analgesic treatment and response, and risk factors for addiction, abuse, and misuse (5.1)
- Respiratory depression can occur at any time during opioid therapy, especially when initiating and following dosage increases with methadone hydrochloride tablets. Consider this risk when selecting an initial dose and when making dose adjustments (2.1, 5.2).
- To convert to methadone hydrochloride tablets from another opioid, use available conversion factors to obtain estimated dose. (2.4)
- Titrate slowly with dose increases no more frequent than every 3 to 5 days. (2.5)
- Periodically reassess patients receiving methadone hydrochloride tablets to evaluate the continued need for opioid analgesics to maintain pain control, for the signs or symptoms of adverse reactions, and for the development of addiction, abuse, or misuse. (2.5)
- Do not not rapidly reduce or abruptly discontinue methadone hydrochloride tablets in a physically dependent patient because rapid reduction or abrupt discontinuation of opioid analgesics has resulted in serious withdrawal symptoms, uncontrolled pain, and suicide. (2.6, 5.16)

Initiation of Detoxification and Maintenance Treatment

- A single dose of 20 to 30 mg may be sufficient to suppress withdrawal syndrome. (2.7)

3 DOSAGE FORMS AND STRENGTHS

Tablets: 10 mg. (3)

4 CONTRAINDICATIONS

- Significant respiratory depression (4)
- Acute or severe bronchial asthma in an unmonitored setting or in the absence of resuscitative equipment (4)
- Known or suspected gastrointestinal obstruction, including paralytic ileus (4)
- Hypersensitivity to methadone (4)

5 WARNINGS AND PRECAUTIONS

- Opioid Induced Hyperalgesia and Allodynia: Opioid-Induced Hyperalgesia (OIH) occurs when an opioid analgesic paradoxically causes an increase in pain, or an increase in sensitivity to pain. If OIH is suspected, carefully consider appropriately decreasing the dose of the current opioid analgesic or opioid rotation. (5.8)
- Serotonin Syndrome: Potentially life-threatening condition could result from concomitant serotonergic drug administration. Discontinue methadone hydrochloride tablets if serotonin syndrome is suspected. (5.9)

- Risk of Life-Threatening Respiratory Depression in Patients with Chronic Pulmonary Disease or in Elderly, Cachectic, or Debilitated Patients: Regularly evaluate closely, particularly during initiation and titration. (5.10)
- Adrenal Insufficiency: If diagnosed, treat with physiologic replacement of corticosteroids, and wean patient off of the opioid. (5.11)
- Severe Hypotension: Regularly evaluate during dose initiation and titration. Avoid use in patients with circulatory shock.(5.12)
- Risks of Use in Patients with Increased Intracranial Pressure, Brain Tumors, Head Injury, or Impaired Consciousness: Regularly evaluate for sedation and respiratory depression. Avoid use of methadone hydrochloride tablets in patients with impaired consciousness or coma. (5.13)

6 ADVERSE REACTIONS

Most common adverse reactions are: lightheadedness, dizziness, sedation, nausea, vomiting, and sweating. (6)

To report SUSPECTED ADVERSE REACTIONS, contact VistaPharm, LLC at 1-888-655-1505 or FDA at 1-800-FDA-1088 or www.fda.gov/medwatch

7 DRUG INTERACTIONS

- Anti-Retroviral Agents: May result in decreased efficacy or, in certain cases, increased toxicity. (7)
- Potentially Arrhythmogenic Agents: Pharmacodynamic interactions may occur. Regularly evaluate patients closely for cardiac conduction changes. (7)
- Mixed Agonist/Antagonist and Partial Agonist Opioid Analgesics: Avoid use with methadone hydrochloride tablets because they may reduce analgesic effect of methadone hydrochloride tablets or precipitate withdrawal symptoms. (5.16, 7)
- Monoamine Oxidase Inhibitors (MAOIs): Can potentiate the effects of methadone. Avoid concomitant use in patients receiving MAOIs or within 14 days of stopping treatment with an MAOI. (7)

8 USE IN SPECIFIC POPULATIONS

- Lactation: Monitor breastfed infants for increased drowsiness and breathing difficulties. (8.2)

FULL PRESCRIBING INFORMATION

WARNING: SERIOUS AND LIFE-THREATENING RISKS FROM USE OF METHADONE HYDROCHLORIDE TABLETS

Addiction, Abuse, and Misuse

Because the use of methadone hydrochloride tablets exposes patients and other users to the risks of opioid addiction, abuse, and misuse, which can lead to overdose and death, assess each patient’s risk prior to prescribing and reassess all patients regularly for the development of these behaviors and conditions [see WARNINGS AND PRECAUTIONS (5.1)].

Life-Threatening Respiratory Depression

Serious, life-threatening, or fatal respiratory depression may occur with use of methadone hydrochloride tablets, especially during initiation or following a dosage increase. To reduce the risk of respiratory depression, proper dosing and titration of methadone hydrochloride tablets are essential [see WARNINGS AND PRECAUTIONS (5.2)].

Accidental Ingestion

Accidental ingestion of even one dose of methadone hydrochloride tablets, especially by children, can result in a fatal overdose of methadone [see Warnings and Precautions (5.2)].

Risks From Concomitant Use With Benzodiazepines Or Other CNS Depressants

Concomitant use of opioids with benzodiazepines or other central nervous system (CNS) depressants, including alcohol, may result in profound sedation, respiratory depression, coma, and death. Reserve concomitant prescribing of methadone hydrochloride tablets and benzodiazepines or other CNS depressants for use in patients for whom alternative treatment options are inadequate [see WARNINGS AND PRECAUTIONS (5.3), DRUG INTERACTIONS (7)].

Neonatal Opioid Withdrawal Syndrome (NOWS)

Neonatal opioid withdrawal syndrome (NOWS) is an expected and treatable outcome of use of methadone hydrochloride tablets during pregnancy. NOWS may be life-threatening if not recognized and treated in the neonate. The balance between the risks of NOWS and the benefits of maternal methadone hydrochloride tablets use may differ based on the risks associated with the mother’s underlying condition, pain, or addiction. Advise the patient of the risk of NOWS so that appropriate planning for management of the neonate can occur [see WARNING AND PRECAUTIONS (5.5)].

Opioid Analgesic Risk Evaluation and Mitigation Strategy (REMS)

Healthcare providers are strongly encouraged to complete a REMS compliant education program and to counsel patients and caregivers on serious risks, safe use, and the importance of reading the Medication Guide with each prescription [see WARNINGS AND PRECAUTIONS (5.6)].

Life-Threatening QT Prolongation

QT interval prolongation and serious arrhythmia (torsades de pointes) have occurred during treatment with methadone. Most cases involve patients being treated for pain with large, multiple daily doses of methadone, although cases have been reported in patients receiving doses commonly used for maintenance treatment of opioid addiction. Closely monitor patients with risk factors for development of prolonged QT interval, a history of cardiac conduction abnormalities, and those taking medications affecting cardiac conduction for changes in cardiac rhythm during initiation and titration of methadone hydrochloride tablets [see WARNINGS AND PRECAUTIONS (5.4)].

Cytochrome P450 Interaction

The concomitant use of methadone hydrochloride tablets with all cytochrome P450 3A4, 2B6, 2C19, 2C9 or 2D6 inhibitors may result in an increase in methadone plasma concentrations, which could cause potentially fatal respiratory depression. In addition, discontinuation of concomitantly used cytochrome P450 3A4, 2B6, 2C19, or 2C9 inducers may also result in an increase in methadone plasma concentration. Follow patients closely for respiratory depression and sedation and consider dosage reduction with any changes of concomitant medications that can result in an increase in methadone levels [see WARNINGS AND PRECAUTIONS (5.7), DRUG INTERACTIONS (7)].

Conditions For Distribution And Use Of Methadone Products For The Treatment Of Opioid Addiction

For detoxification and maintenance of opioid dependence, methadone should be administered in accordance with the treatment standards cited in 42 CFR Section 8, including limitations on unsupervised administration [see INDICATIONS AND USAGE (1), DOSAGE AND ADMINISTRATION (2.1)].

RECENT MAJOR CHANGES

Boxed Warning 09/2018

Warnings and Precautions (5) 09/2018

1 INDICATIONS AND USAGE

Methadone hydrochloride tablets is indicated for the:

1. Management of severe and persistent pain that requires an opioid analgesic and that cannot be adequately treated with alternative options, including immediate-release opioids.
  Limitations of Use
  - Because of the risks of addiction, abuse, misuse, overdose, and death, which can occur at any dosage or duration and persist over the course of therapy [see WARNINGS AND PRECAUTIONS (5.1)], reserve opioid analgesics, including methadone hydrochloride tablets, for use in patients for whom alternative analgesic treatment options are ineffective, not tolerated, or would be otherwise inadequate to provide sufficient management of pain.
  - Methadone hydrochloride tablets are not indicated as an as-needed (prn) analgesic. (1)
2. Detoxification treatment of opioid addiction (heroin or other morphine-like drugs).
3. Maintenance treatment of opioid addiction (heroin or other morphine-like drugs), in conjunction with appropriate social and medical services.
  Limitations of Use
  Methadone products used for the treatment of opioid addiction in detoxification or maintenance programs are subject to the conditions for distribution and use required under 42 CFR 8.12 [see DOSAGE AND ADMINISTRATION (2.1)].

2 DOSAGE AND ADMINISTRATION

2.1 Conditions for Distribution and Use of Methadone Products for the Treatment of Opioid Addiction

Code of Federal Regulations, Title 42, Sec 8: Methadone products when used for the treatment of opioid addiction in detoxification or maintenance programs, shall be dispensed only by opioid treatment programs (and agencies, practitioners or institutions by formal agreement with the program sponsor) certified by the Substance Abuse and Mental Health Services Administration and approved by the designated state authority. Certified treatment programs shall dispense and use methadone in oral form only and according to the treatment requirements stipulated in the Federal Opioid Treatment Standards (42 CFR 8.12). See below for important regulatory exceptions to the general requirement for certification to provide opioid agonist treatment.

Failure to abide by the requirements in these regulations may result in criminal prosecution, seizure of the drug supply, revocation of the program approval, and injunction precluding operation of the program.

Regulatory Exceptions to the General Requirement for Certification to Provide Opioid Agonist Treatment:

- During inpatient care, when the patient was admitted for any condition other than concurrent opioid addiction (pursuant to 21 CFR 1306.07(c)), to facilitate the treatment of the primary admitting diagnosis).
- During an emergency period of no longer than 3 days while definitive care for the addiction is being sought in an appropriately licensed facility (pursuant to 21 CFR 1306.07(b)).

2.2 Important General Information

- The peak respiratory depressant effect of methadone occurs later and persists longer than its peak therapeutic effect.
- A high degree of opioid tolerance does not eliminate the possibility of methadone overdose, iatrogenic or otherwise. Deaths have been reported during conversion to methadone from chronic, high-dose treatment with other opioid agonists and during initiation of methadone treatment of addiction in subjects previously abusing high doses of other agonists.
- With repeated dosing, methadone is retained in the liver and then slowly released, prolonging the duration of potential toxicity.
- Methadone has a narrow therapeutic index, especially when combined with other drugs.

2.3 Patient Access to an Opioid Overdose Reversal Agent for the Emergency Treatment of Opioid Overdose

Inform patients and caregivers about opioid overdose reversal agents (e.g., naloxone, nalmefene) and discuss the importance of having access to an opioid overdose reversal agent. [see WARNINGS AND PRECAUTIONS (5.1), OVERDOSAGE (10)].

For Patients Being Treated for Pain

Discuss the importance of having access to an opioid overdose reversal agent, especially if the patient has risk factors for overdose (e.g., concomitant use of CNS depressants, a history of opioid use disorder, or prior opioid overdose) or if there are household members (including children) or other close contacts at risk for accidental ingestion or opioid overdose. The presence of risk factors for overdose should not prevent the management of pain in any patient [see WARNINGS AND PRECAUTIONS (5.1, 5.2,5.3)].

For Patients Being Treated for Opioid Addiction

Because patients being treated for opioid use disorder have the potential for relapse, putting them at risk for opioid overdose, strongly consider recommending or prescribing an overdose reversal agent for the emergency treatment of opioid overdose, both when initiating and renewing treatment with methadone hydrochloride tablets. Advise patients and caregivers that an opioid overdose reversal agent, such as naloxone or nalmefene may also be administered for a known or suspected overdose with methadone hydrochloride tablets itself [see OVERDOSAGE (10)].

For patients being treated with methadone (regardless of indication), also consider prescribing or recommending such an agent if the patient has household members (including children) or other close contacts at risk for accidental ingestion or overdose.

Discuss the options for obtaining an opioid overdose reversal agent (e.g., prescription, over-the-counter, or as part of a community-based program) [see WARNINGS AND PRECAUTIONS (5.2)].

There are important differences among the opioid overdose reversal agents, such as route of administration, product strength, approved patient age range, and pharmacokinetics. Be familiar with these differences, as outlined in the approved labeling for those products, prior to recommending or prescribing such an agent.

2.4 Methadone Hydrochloride Tablets for Management of Pain

Important Dosage and Administration Information

Methadone hydrochloride tablets should be prescribed only by healthcare professionals who are knowledgeable about the use of extended-release/long-acting opioids and how to mitigate the associated risks.

Consider the following important factors that differentiate methadone from other opioid analgesics:

- There is high interpatient variability in absorption, metabolism, and relative analgesic potency of methadone. Population-based equianalgesic conversion ratios between methadone and other opioids are not accurate when applied to individuals.
- The duration of analgesic action of methadone is 4 to 8 hours (based on single-dose studies) but the plasma elimination half-life is 8 to 59 hours.
- With repeated dosing, the potency of methadone increases due to systemic accumulation.
- Steady-state plasma concentrations and full analgesic effects are not attained until at least 3 to 5 days on a dose, and may take longer in some patients.

Use the lowest effective dosage for the shortest duration of time consistent with individual patient treatment goals [see WARNINGS AND PRECAUTIONS (5)]. Because the risk of overdose increases as opioid doses increase, reserve titration to higher doses of methadone hydrochloride tablets for patients in whom lower doses are insufficiently effective and in whom the expected benefits of using a higher dose opioid clearly outweigh the substantial risks.

Initiate the dosing regimen for each patient individually, taking into account the patient’s underlying cause and severity of pain, prior analgesic treatment and response, and risk factors for addiction, abuse, and misuse [see WARNINGS AND PRECAUTIONS (5.1)]

Respiratory depression can occur at any time during opioid therapy, especially when initiating and following dosage increases with methadone hydrochloride tablets. Consider this risk when selecting an initial dose and when making dose adjustments [see WARNINGS AND PRECAUTIONS (5)].

Conversion from Other Oral Opioids to Methadone Hydrochloride Tablets: When methadone hydrochloride tablets therapy is initiated, discontinue all other opioid analgesics other than those used on an as needed basis for breakthrough pain when appropriate. Deaths have occurred in opioid-tolerant patients during conversion to methadone.

The potency of methadone relative to other opioid analgesics is nonlinear and increases with increasing dose. Table 1 provides an estimated conversion factor for use when converting patients from another opioid to methadone. Because of the high inter-patient variability in absorption, metabolism, and relative potency, it is critical to avoid overestimating the methadone dose which can lead to fatal respiratory depression. It is safer to underestimate a patient’s 24-hour methadone dosage and provide rescue medication (e.g., immediate-release opioid) than to overestimate the 24-hour methadone dosage and manage an adverse reaction due to an overdose.

Consider the following when using the information in Table 1:

- This is not a table of equianalgesic doses.
- The conversion factors in this table are only for the conversion from another oral opioid analgesic to methadone hydrochloride tablets.
- The table cannot be used to convert from methadone hydrochloride tablets to another opioid. Doing so will result in an overestimation of the dose of the new opioid and may result in fatal overdose.

Table 1: Conversion Factors to Methadone Hydrochloride Tablets

Total Daily Baseline Oral Morphine Equivalent Dose | Estimated Daily Oral Methadone Requirement as Percent of Total Daily Morphine Equivalent Dose
< 100 mg | 20% to 30%
100 to 300 mg | 10% to 20%
300 to 600 mg | 8% to 12%
600 mg to 1000 mg | 5% to 10%
> 1000 mg | < 5 %

To calculate the estimated methadone hydrochloride tablets dose using Table 1:

- For patients on a single opioid, sum the current total daily dose of the opioid, convert it to a Morphine Equivalent Dose according to specific conversion factor for that specific opioid, then multiply the Morphine Equivalent Dose by the corresponding percentage in the above table to calculate the approximate oral methadone daily dose. Divide the total daily methadone dose derived from the table above to reflect the intended dosing schedule (i.e., for administration every 8 hours, divide total daily methadone dose by 3).
- For patients on a regimen of more than one opioid, calculate the approximate oral methadone dose for each opioid and sum the totals to obtain the approximate total methadone daily dose. Divide the total daily methadone dose derived from the table above to reflect the intended dosing schedule (i.e., for administration every 8 hours, divide total daily methadone dose by 3).
- For patients on a regimen of fixed-ratio opioid/non-opioid analgesic products, use only the opioid component of these products in the conversion.

Always round the dose down, if necessary, to the appropriate methadone hydrochloride tablets strength(s) available.

Example conversion from a single opioid to methadone hydrochloride tablets:

Step 1:

Sum the total daily dose of the opioid (in this case, Morphine Extended Release Tablets 50 mg twice daily)

50 mg Morphine Extended Release Tablets 2 times daily = 100 mg total daily dose of Morphine

Step 2:

Calculate the approximate equivalent dose of methadone hydrochloride tablets based on the total daily dose of Morphine using Table 1.

100 mg total daily dose of Morphine x 15% (10% to 20% per Table 1) = 15 mg methadone hydrochloride tablets daily

Step 3:

Calculate the approximate starting dose of methadone hydrochloride tablets to be given every 12 hours. Round down, if necessary, to the appropriate methadone hydrochloride tablets strengths available.

15 mg daily / 2 = 7.5 mg methadone hydrochloride tablets every 12 hours
Then 7.5 mg is rounded down to 5 mg methadone hydrochloride tablets every 12 hours

Close observation and frequent titration are warranted until pain management is stable on the new opioid. Monitor patients for signs and symptoms of opioid withdrawal or for signs of over-sedation/toxicity after converting patients to methadone hydrochloride tablets.

Conversion from Parenteral Methadone to Methadone Hydrochloride Tablets: Use a conversion ratio of 1:2 mg for parenteral to oral methadone (e.g., 5 mg parenteral methadone to 10 mg oral methadone).

2.5 Titration and Maintenance of Therapy for Pain

Individually titrate methadone hydrochloride tablets to a dose that provides adequate analgesia and minimizes adverse reactions. Continually reevaluate patients receiving methadone hydrochloride tablets to assess the maintenance of pain control, signs and symptoms of opioid withdrawal, and other adverse reactions, as well as to reassess for the development of addiction, abuse, or misuse [see WARNINGS AND PRECAUTIONS (5.1, 5.16)]. Frequent communication is important among the prescriber, other members of the healthcare team, the patient, and the caregiver/family during periods of changing analgesic requirements, including initial titration. During use of opioid therapy for an extended period of time, periodically reassess the continued need for the use of opioid analgesics.

Patients who experience breakthrough pain may require a dose increase of methadone hydrochloride tablets, or may need rescue medication with an appropriate dose of an immediate-release analgesic. If the level of pain increases after dosage stabilization, attempt to identify the source of increased pain before increasing the methadone hydrochloride tablets dosage.

Because of individual variability in the pharmacokinetic profile (i.e., terminal half-life (T1/2) from 8 to 59 hours in different studies [see CLINICAL PHARMACOLOGY (12.3)], titrate methadone hydrochloride tablets slowly, with dose increases no more frequent than every 3 to 5 days. However, because of this high variability, some patients may require substantially longer periods between dose increases (up to 12 days). Monitor patients closely for the development of potentially life-threatening adverse reactions (e.g., CNS and respiratory depression).

If after increasing the dosage, unacceptable opioid-related adverse reactions are observed (including an increase in pain after dosage increase), consider reducing the dosage [see WARNINGS AND PRECAUTIONS (5)]. Adjust the dose to obtain an appropriate balance between management of pain and opioid-related adverse reactions.

2.6 Safe Reduction or Discontinuation of Methadone Hydrochloride Tablets for Pain

Do not rapidly reduce or abruptly discontinue methadone hydrochloride tablets in patients who may be physically dependent on opioids. Rapid reduction or abrupt discontinuation of opioid analgesics in patients who are physically dependent on opioids has resulted in serious withdrawal symptoms, uncontrolled pain, and suicide. Rapid reduction or abrupt discontinuation has also been associated with attempts to find other sources of opioid analgesics, which may be confused with drug-seeking for abuse. Patients may also attempt to treat their pain or withdrawal symptoms with illicit opioids, such as heroin, and other substances.

When a decision has been made to decrease the dose or discontinue therapy in an opioid-dependent patient taking methadone hydrochloride tablets, there are a variety of factors that should be considered, including the total daily dose of opioid (including methadone hydrochloride tablets) the patient has been taking, the duration of treatment, the type of pain being treated, and the physical and psychological attributes of the patient. It is important to ensure ongoing care of the patient and to agree on an appropriate tapering schedule and follow-up plan so that patient and provider goals and expectations are clear and realistic. When opioid analgesics are being discontinued due to a suspected substance use disorder, evaluate and treat the patient, or refer for evaluation and treatment of the substance use disorder. Treatment should include evidence-based approaches, such as medication assisted treatment of opioid use disorder. Complex patients with co-morbid pain and substance use disorders may benefit from referral to a specialist.

There are no standard opioid tapering schedules that are suitable for all patients. Good clinical practice dictates a patient-specific plan to taper the dose of the opioid gradually. For patients on methadone hydrochloride tablets who are physically opioid-dependent, initiate the taper by a small enough increment (e.g., no greater than 10% to 25% of the total daily dose) to avoid withdrawal symptoms, and proceed with dose-lowering at an interval of every 2 to 4 weeks. Patients who have been taking opioids for briefer periods of time may tolerate a more rapid taper.

It may be necessary to provide the patient with lower dosage strengths to accomplish a successful taper. Reassess the patient frequently to manage pain and withdrawal symptoms, should they emerge. Common withdrawal symptoms include restlessness, lacrimation, rhinorrhea, yawning, perspiration, chills, myalgia, and mydriasis. Other signs and symptoms also may develop, including irritability, anxiety, backache, joint pain, weakness, abdominal cramps, insomnia, nausea, anorexia, vomiting, diarrhea, or increased blood pressure, respiratory rate, or heart rate. If withdrawal symptoms arise, it may be necessary to pause the taper for a period of time or raise the dose of the opioid analgesic to the previous dose, and then proceed with a slower taper. In addition, evaluate patients for any changes in mood, emergence of suicidal thoughts, or use of other substances.

When managing patients taking opioid analgesics, particularly those who have been treated for an extended period of time, and/or with high doses for chronic pain, ensure that a multimodal approach to pain management, including mental health support (if needed), is in place prior to initiating an opioid analgesic taper. A multimodal approach to pain management may optimize the treatment of chronic pain, as well as assist with the successful tapering of the opioid analgesic [see WARNINGS AND PRECAUTIONS (5.16), DRUG ABUSE AND DEPENDENCE (9.3)].

2.7 Induction/Initial Dosing for Detoxification and Maintenance Treatment of Opioid Addiction

For detoxification and maintenance of opioid dependence methadone should be administered in accordance with the treatment standards cited in 42 CFR Section 8.12, including limitations on unsupervised administration.

Administer the initial methadone dose under supervision, when there are no signs of sedation or intoxication, and the patient shows symptoms of withdrawal. An initial single dose of 20 to 30 mg of methadone hydrochloride tablets will often be sufficient to suppress withdrawal symptoms. The initial dose should not exceed 30 mg.

To make same-day dosing adjustments, have the patient wait 2 to 4 hours for further evaluation, when peak levels have been reached. Provide an additional 5 to 10 mg of methadone hydrochloride tablets if withdrawal symptoms have not been suppressed or if symptoms reappear.

The total daily dose of methadone hydrochloride tablets on the first day of treatment should not ordinarily exceed 40 mg. Adjust the dose over the first week of treatment based on control of withdrawal symptoms at the time of expected peak activity (e.g., 2 to 4 hours after dosing). When adjusting the dose, keep in mind that methadone levels will accumulate over the first several days of dosing; deaths have occurred in early treatment due to the cumulative effects. Instruct patients that the dose will “hold” for a longer period of time as tissue stores of methadone accumulate.

Use lower initial doses for patients whose tolerance is expected to be low at treatment entry. Any patient who has not taken opioids for more than 5 days may no longer be tolerant. Do not determine initial doses based on previous treatment episodes or dollars spent per day on illicit drug use.

During the induction phase of methadone maintenance treatment, patients are being withdrawn from opioids and may have opioid withdrawal symptoms. Monitor patients for signs and symptoms of opioid withdrawal including: lacrimation, rhinorrhea, sneezing, yawning, excessive perspiration, goose-flesh, fever, chilling alternating with flushing, restlessness, irritability, weakness, anxiety, depression, dilated pupils, tremors, tachycardia, abdominal cramps, body aches, involuntary twitching and kicking movements, anorexia, nausea, vomiting, diarrhea, intestinal spasms, and weight loss and consider dose adjustment as indicated.

Short-term Detoxification

For a brief course of stabilization followed by a period of medically supervised withdrawal, titrate the patient to a total daily dose of about 40 mg in divided doses to achieve an adequate stabilizing level. After 2 to 3 days of stabilization, gradually decrease the dose of methadone hydrochloride tablets. Decrease the dose of methadone hydrochloride tablets on a daily basis or at 2-day intervals, keeping the amount of methadone hydrochloride tablets sufficient to keep withdrawal symptoms at a tolerable level. Hospitalized patients may tolerate a daily reduction of 20% of the total daily dose. Ambulatory patients may need a slower schedule.

2.8 Titration and Maintenance Treatment of Opioid Dependence

Titrate patients in maintenance treatment to a dose that prevents opioid withdrawal symptoms for 24 hours, reduces drug hunger or craving, and blocks or attenuates the euphoric effects of self-administered opioids, ensuring that the patient is tolerant to the sedative effects of methadone. Most commonly, clinical stability is achieved at doses between 80 to 120 mg/day. During prolonged administration of methadone, monitor patients for persistent constipation and manage accordingly.

2.9 Medically Supervised Withdrawal after a Period of Maintenance Treatment for Opioid Addiction

There is considerable variability in the appropriate rate of methadone taper in patients choosing medically supervised withdrawal from methadone treatment. Dose reductions should generally be less than 10% of the established tolerance or maintenance dose, and 10 to 14-day intervals should elapse between dose reductions. Apprise patients of the high risk of relapse to illicit drug use associated with discontinuation of methadone maintenance treatment.

2.10 Risk of Relapse in Patients on Methadone Maintenance Treatment of Opioid Addiction

Abrupt opioid discontinuation can lead to development of opioid withdrawal symptoms [see DRUG ABUSE AND DEPENDENCE (9.3)]. Opioid withdrawal symptoms have been associated with an increased risk of relapse to illicit drug use in susceptible patients.

2.11 Considerations for Management of Acute Pain during Methadone Maintenance Treatment

Patients in methadone maintenance treatment for opioid dependence who experience physical trauma, postoperative pain or other acute pain cannot be expected to derive analgesia from their existing dose of methadone. Such patients should be administered analgesics, including opioids, in doses that would otherwise be indicated for non-methadone-treated patients with similar painful conditions. When opioids are required for management of acute pain in methadone maintenance patients, somewhat higher and/or more frequent doses will often be required than would be the case for non-tolerant patients due to the opioid tolerance induced by methadone.

2.12 Dosage Adjustment during Pregnancy

Methadone clearance may be increased during pregnancy. During pregnancy, a woman’s methadone dose may need to be increased or the dosing interval decreased. [see USE IN SPECIFIC POPULATIONS (8.1)].

3 DOSAGE FORMS AND STRENGTHS

10 mg Tablets: White, round, biconvex tablets, scored on one side and debossed with “N” above the score and “128” below the score and plain on the other side.

4 CONTRAINDICATIONS

Methadone hydrochloride tablets are contraindicated in patients with:

- Significant respiratory depression [see WARNINGS AND PRECAUTIONS (5.2)].
- Acute or severe bronchial asthma in an unmonitored setting or in the absence of resuscitative equipment [see WARNINGS AND PRECAUTIONS (5.10)].
- Known or suspected gastrointestinal obstruction, including paralytic ileus [see WARNINGS AND PRECAUTIONS (5.14)].
- Hypersensitivity (e.g., anaphylaxis) to methadone [see ADVERSE REACTIONS (6)].

5 WARNINGS AND PRECAUTIONS

5.1 Addiction, Abuse and Misuse

Methadone hydrochloride tablets contain methadone, a Schedule II controlled substance. As an opioid, methadone hydrochloride tablets expose users to the risks of addiction, abuse, and misuse.As long-acting opioids such as methadone hydrochloride tablets have pharmacological effects over an extended period of time, there is a greater risk for overdose and death [see DRUG ABUSE AND DEPENDENCE (9)].

Although the risk of addiction in any individual is unknown, it can occur in patients appropriately prescribed methadone hydrochloride tablets. Addiction can occur at recommended doses and if the drug is misused or abused. The risk of opioid-related overdose or overdose-related death is increased with higher opioid doses, and this risk persists over the course of therapy. In postmarketing studies, addiction, abuse, misuse, and fatal and non-fatal opioid overdose were observed in patients with long-term opioid use [see ADVERSE REACTIONS (6)].

Assess each patient’s risk for opioid addiction, abuse, or misuse prior to prescribing methadone hydrochloride tablets, and reassess all patients receiving methadone hydrochloride tablets for the development of these behaviors and conditions. Risks are increased in patients with a personal or family history of substance abuse (including drug or alcohol abuse or addiction) or mental illness (e.g., major depression). The potential for these risks should not, however, prevent the proper management of pain in any given patient. Patients at increased risk may be prescribed opioids such as methadone hydrochloride tablets, but use in such patients necessitates intensive counseling about the risks and proper use of methadone hydrochloride tablets along with the frequent reevaluation for signs of addiction, abuse, and misuse. Consider recommending or prescribing an opioid overdose reversal agent [see DOSAGE AND ADMINISTRATION (2.3), WARNINGS AND PRECAUTIONS (5.2)].

Abuse or misuse of methadone hydrochloride tablets by crushing, chewing, snorting, or injecting the dissolved product will result in the uncontrolled delivery of the methadone and can result in overdose and death [see OVERDOSAGE (10)].

Opioids are sought for nonmedical use and are subject to diversion from legitimate prescribed use. Consider these risks when prescribing or dispensing methadone hydrochloride tablets. Strategies to reduce these risks include prescribing the drug in the smallest appropriate quantity and advising the patient on careful storage of the drug during the course of treatment and proper disposal of unused drug. Contact local state professional licensing board or state-controlled substances authority for information on how to prevent and detect abuse or diversion of this product.

5.2 Life-Threatening Respiratory Depression

Serious, life-threatening, or fatal respiratory depression has been reported with the use of methadone, even when used as recommended. The peak respiratory depressant effect of methadone occurs later, and persists longer than the peak analgesic effect. Respiratory depression from opioid use, if not immediately recognized and treated, may lead to respiratory arrest and death. Management of respiratory depression may include close observation, supportive measures, and use of opioid overdose reversal agents, depending on the patient’s clinical status [see OVERDOSAGE (10)]. Carbon dioxide (CO2) retention from opioid-induced respiratory depression can exacerbate the sedating effects of opioids.

While serious, life-threatening, or fatal respiratory depression can occur at any time during the use of methadone hydrochloride tablets, the risk is greatest during the initiation of therapy or following a dosage increase. The peak respiratory depressant effect of methadone occurs later, and persists longer than the peak analgesic effect, especially during the initial dosing period. Regularly evaluate patients for respiratory depression, when initiating therapy with methadone hydrochloride tablets and following dose increases.

To reduce the risk of respiratory depression, proper dosing and titration of methadone hydrochloride tablets are essential [see DOSAGE AND ADMINISTRATION (2.4, 2.5)]. Overestimating the methadone hydrochloride tablets dosage when converting patients from another opioid product can result in fatal overdose with the first dose.

Accidental ingestion of even one dose of methadone hydrochloride tablets, especially by children, can result in respiratory depression and death due to an overdose of methadone.

Educate patients and caregivers on how to recognize respiratory depression and emphasize the importance of calling 911 or getting emergency medical help right away in the event of a known or suspected overdose [see PATIENT COUNSELING INFORMATION (17)].

Opioids can cause sleep-related breathing disorders including central sleep apnea (CSA) and sleep-related hypoxemia. Opioid use increases the risk of CSA in a dose-dependent fashion. In patients who present with CSA, consider decreasing the opioid dosage using best practices for opioid taper [see DOSAGE AND ADMINISTRATION (2.5)].

Patient Access to an Opioid Overdose Reversal Agent for the Emergency Treatment of Opioid Overdose:

Inform patients and caregivers about opioid overdose reversal agents (e.g., naloxone, nalmefene) and discuss the importance of having access to an opioid overdose reversal agent.

For Patients Being Treated for Pain

Discuss the importance of having access to an opioid overdose reversal agent, especially if the patient has risk factors for overdose e.g., concomitant use of CNS depressants, a history of opioid use disorder, or prior opioid overdose) or if there are household members (including children) or other close contacts at risk for accidental ingestion or opioid overdose. The presence of risk factors for overdose should not prevent the proper management of pain in any given patient. [see DOSAGE AND ADMINISTRATION (2.3), WARNINGS AND PRECAUTIONS (5.1, 5.3), OVERDOSAGE (10)].

For Patients Being Treated for Opioid Addiction

Because patients being treated for opioid use disorder have the potential for relapse, putting them at risk for opioid overdose, strongly consider recommending or prescribing an opioid overdose reversal agent for the emergency treatment of an opioid overdose, both when initiating and renewing treatment with methadone hydrochloride tablets. Advise patients and caregivers that an opioid overdose reversal agent, such as naloxone or nalmefene, may also be administered for a known or suspected overdose with methadone hydrochloride tablets itself [see OVERDOSAGE (10)].

For patients being treated with methadone (regardless of indication), also consider prescribing or recommending such an agent if the patient has household members (including children) or other close contacts at risk for accidental ingestion or overdose.

Discuss the options for obtaining an opioid overdose reversal agent (e.g., prescription, over-the-counter, or as part of a community-based program).

There are important differences among the opioid overdose reversal agents, such as route of administration, product strength, approved patient age range, and pharmacokinetics. Be familiar with these differences, as outlined in the approved labeling for those products, prior to recommending or prescribing such an agent.

Educate patients and caregivers on how to recognize respiratory depression, and how to use an opioid overdose reversal agent for the emergency treatment of opioid overdose. Emphasize the importance of calling 911 or getting emergency medical help, even if an opioid overdose reversal agent is administered.

5.3 Risks from Concomitant Use with Benzodiazepines or Other CNS Depressants

Profound sedation, respiratory depression, coma, and death may result from the concomitant use of methadone hydrochloride tablets with benzodiazepines and/or other CNS depressants (e.g., alcohol, non-benzodiazepine sedatives/hypnotics, anxiolytics, tranquilizers, muscle relaxants, general anesthetics, antipsychotics, gabapentinoids [gabapentin or pregabalin], and other opioids).

For Patients Being Treated for Pain

Because of these risks, reserve concomitant prescribing of these drugs for use in patients for whom alternative treatment options are inadequate.

Observational studies have demonstrated that concomitant use of opioid analgesics and benzodiazepines increases the risk of drug-related mortality compared to use of opioid analgesics alone. Because of similar pharmacological properties, it is reasonable to expect similar risk with the concomitant use of other CNS depressant drugs with opioid analgesics [see DRUG INTERACTIONS (7)].

If the decision is made to prescribe a benzodiazepine or other CNS depressant concomitantly with an opioid analgesic, prescribe the lowest effective dosages and minimum durations of concomitant use. In patients already receiving an opioid analgesic, prescribe a lower initial dose of the benzodiazepine or other CNS depressant than indicated in the absence of an opioid, and titrate based on clinical response. If an opioid analgesic is initiated in a patient already taking a benzodiazepine or other CNS depressant, prescribe a lower initial dose of the opioid analgesic, and titrate based on clinical response. Inform patients and caregivers of this potential interaction, educate them on the signs and symptoms of respiratory depression (including sedation).

If concomitant use is warranted, consider recommending of prescribing an opioid overdose reversal agent [see DOSAGE AND ADMINISTRATION (2.3), WARNINGS AND PRECAUTIONS (5.2)].

Advise both patients and caregivers about the risks of respiratory depression and sedation when methadone hydrochloride tablets are used with benzodiazepines or other CNS depressants (including alcohol and illicit drugs). Advise patients not to drive or operate heavy machinery until the effects of concomitant use of the benzodiazepine or other CNS depressant have been determined. Screen patients for risk of substance use disorders, including opioid abuse and misuse, and warn them of the risk for overdose and death associated with the use of additional CNS depressants including alcohol and illicit drugs [see DRUG INTERACTIONS (7) AND PATIENT COUNSELING INFORMATION (17)].

For Patients Being Treated for Opioid Addiction

Concomitant use of methadone and benzodiazepines or other CNS depressants increases the risk of adverse reactions including overdose and death. Medication-assisted treatment of opioid use disorder, however, should not be categorically denied to patients taking these drugs. Prohibiting or creating barriers to treatment can pose an even greater risk of morbidity and mortality due to the opioid use disorder alone.

As a routine part of orientation to methadone treatment, educate patients about the risks of concomitant use of benzodiazepines, sedatives, opioid analgesics, or alcohol.

Develop strategies to manage use of prescribed or illicit benzodiazepines or other CNS depressants at admission to methadone treatment, or if it emerges as a concern during treatment. Adjustments to induction procedures and additional monitoring may be required. There is no evidence to support dose limitations or arbitrary caps of methadone as a strategy to address benzodiazepine use in methadone-treated patients. However, if a patient is sedated at the time of methadone dosing, ensure that a medically-trained healthcare provider evaluates the cause of sedation, and delays or omits the methadone dose if appropriate.

Cessation of benzodiazepines or other CNS depressants is preferred in most cases of concomitant use. In some cases monitoring in a higher level of care for taper may be appropriate. In others, gradually tapering a patient off a prescribed benzodiazepine or other CNS depressant or decreasing to the lowest effective dose may be appropriate.

For patients in methadone treatment, benzodiazepines are not the treatment of choice for anxiety or insomnia. Before co-prescribing benzodiazepines, ensure that patients are appropriately diagnosed and consider alternative medications and non-pharmacologic treatments to address anxiety or insomnia. Ensure that other healthcare providers prescribing benzodiazepines or other CNS depressants are aware of the patient’s methadone treatment and coordinate care to minimize the risks associated with concomitant use.

If concomitant use is warranted, strongly consider recommending or prescribing an opioid overdose reversal agent, as is recommended for all patients in methadone treatment for opioid use disorder [see DOSAGE AND ADMINISTRATION (2.3), WARNINGS AND PRECAUTIONS (5.2)].

In addition, take measures to confirm that patients are taking the medications prescribed and not diverting or supplementing with illicit drugs. Toxicology screening should test for prescribed and illicit benzodiazepines [see DRUG INTERACTIONS (7)].

5.4 Life-Threatening QT Prolongation

Cases of QT interval prolongation and serious arrhythmia (torsades de pointes) have been observed during treatment with methadone. These cases appear to be more commonly associated with, but not limited to, higher dose treatment (> 200 mg/day). Most cases involve patients being treated for pain with large, multiple daily doses of methadone, although cases have been reported in patients receiving doses commonly used for maintenance treatment of opioid addiction. In most patients on the lower doses typically used for maintenance, concomitant medications and/or clinical conditions such as hypokalemia were noted as contributing factors. However, the evidence strongly suggests that methadone possesses the potential for adverse cardiac conduction effects in some patients. The effects of methadone on the QT interval have been confirmed in in vivo laboratory studies, and methadone has been shown to inhibit cardiac potassium channels in in vitro studies.

Closely monitor patients with risk factors for development of prolonged QT interval (e.g., cardiac hypertrophy, concomitant diuretic use, hypokalemia, hypomagnesemia), a history of cardiac conduction abnormalities, and those taking medications affecting cardiac conduction. QT prolongation has also been reported in patients with no prior cardiac history who have received high doses of methadone.

Evaluate patients developing QT prolongation while on methadone treatment for the presence of modifiable risk factors, such as concomitant medications with cardiac effects, drugs that might cause electrolyte abnormalities, and drugs that might act as inhibitors of methadone metabolism.

Only initiate methadone hydrochloride tablets therapy for pain in patients for whom the anticipated benefit outweighs the risk of QT prolongation and development of dysrhythmias that have been reported with high doses of methadone.

The use of methadone in patients already known to have a prolonged QT interval has not been systematically studied.

5.5 Neonatal Opioid Withdrawal Syndrome

Neonatal opioid withdrawal syndrome (NOWS) is an expected and treatable outcome of use of opioids for an extended period of time during pregnancy.

The balance between the risks of NOWS and the benefits of maternal methadone hydrochloride tablet use may differ based on the risks associated with the mother’s underlying condition, pain or addiction, and the risks of the alternative treatments.

- For management of pain, prescribers should discuss all available treatment options with females of reproductive potential, including non-opioid and non-pharmacologic options.

- Untreated opioid addiction often results in continued or relapsing illicit opioid use and is associated with poor pregnancy outcomes. NOWS can result from in utero exposure to opioids regardless of the source. Therefore, prescribers should discuss the importance and benefits of management of opioid addiction throughout pregnancy.

5.6 Opioid Analgesic Risk Evaluation and Mitigation Strategy (REMS)

To ensure that the benefits of opioid analgesics outweigh the risks of addiction, abuse, and misuse, the Food and Drug Administration (FDA) has required a Risk Evaluation and Mitigation Strategy (REMS) for these products. Under the requirements of the REMS, drug companies with approved opioid analgesic products must make REMS-compliant education programs available to healthcare providers. Healthcare providers are strongly encouraged to do all of the following:

- Complete a REMS-compliant education program offered by an accredited provider of continuing education (CE) or another education program that includes all the elements of the FDA Education Blueprint for Health Care Providers Involved in the Management or Support of Patients with Pain.
- Discuss the safe use, serious risks, and proper storage and disposal of opioid analgesics with patients and/or their caregivers every time these medicines are prescribed. The Patient Counseling Guide (PCG) can be obtained at this link: www.fda.gov/OpioidAnalgesicREMSPCG.
- Emphasize to patients and their caregivers the importance of reading the Medication Guide that they will receive from their pharmacist every time an opioid analgesic is dispensed to them.
- Consider using other tools to improve patient, household, and community safety, such as patient-prescriber agreements that reinforce patient-prescriber responsibilities.

To obtain further information on the opioid analgesic REMS and for a list of accredited REMS CME/CE, call 1-800-503-0784, or log on to www.opioidanalgesicrems.com. The FDA Blueprint can be found at www.fda.gov/OpioidAnalgesicREMSBlueprint.

5.7 Risks of Concomitant Use of Cytochrome P450 3A4, 2B6, 2C19, 2C9, or 2D6 Inhibitors or Discontinuation of P450 3A4, 2B6, 2C19, or 2C9 Inducers

Concomitant use of methadone hydrochloride tablets with CYP3A4, CYP2B6, CYP2C19, CYP2C9, or CYP2D6 inhibitors, may increase plasma concentrations of methadone, prolong opioid adverse reactions, and may cause potentially fatal respiratory depression, particularly when an inhibitor is added after a stable dosage of methadone hydrochloride tablets is achieved. Similarly, discontinuation of concomitant CYP3A4, CYP2B6, CYP2C19, or CYP2C9 inducers in methadone hydrochloride tablet-treated patients may increase methadone plasma concentrations resulting in fatal respiratory depression. Consider dosage reduction of methadone hydrochloride tablets when using concomitant CYP3A4, CYP2B6, CYP2C19, CYP2C9 or CYP2D6 inhibitors or discontinuing CYP3A4, CYP2B6, CYP2C19, or CYP2C9 inducers in methadone-treated patients, and evaluate patients closely at frequent intervals for signs and symptoms of respiratory depression and sedation [see DRUG INTERACTIONS (7)].

Addition of CYP3A4, CYP2B6, CYP2C19, or CYP2C9 inducers or discontinuation of CYP3A4, CYP2B6, CYP2C19, CYP2C9, or CYP2D6 inhibitors in patients treated with methadone hydrochloride tablets may decrease methadone plasma concentrations, reducing efficacy and may lead to opioid withdrawal symptoms in patients physically dependent on methadone. When using methadone hydrochloride tablets with CYP3A4, CYP2B6, CYP2C19, or CYP2C9 inducers or discontinuing CYP3A4, CYP2B6, CYP2C19, CYP2C9, or CYP2D6 inhibitors, assess patients for signs or symptoms of opioid withdrawal and consider increasing the methadone hydrochloride tablets dosage as needed [see DRUG INTERACTIONS (7)].

5.8 Opioid-Induced Hyperalgesia and Allodynia

Opioid-Induced Hyperalgesia (OIH) occurs when an opioid analgesic paradoxically causes an increase in pain, or an increase in sensitivity to pain. This condition differs from tolerance, which is the need for increasing doses of opioids to maintain a defined effect [see DEPENDENCE (9.3)]. Symptoms of OIH include (but may not be limited to) increased levels of pain upon opioid dosage increase, decreased levels of pain upon opioid dosage decrease, or pain from ordinarily non-painful stimuli (allodynia). These symptoms may suggest OIH only if there is no evidence of underlying disease progression, opioid tolerance, opioid withdrawal, or addictive behavior.

Cases of OIH have been reported, both with short-term and longer-term use of opioid analgesics. Though the mechanism of OIH is not fully understood, multiple biochemical pathways have been implicated. Medical literature suggests a strong biologic plausibility between opioid analgesics and OIH and allodynia. If a patient is suspected to be experiencing OIH, carefully consider appropriately decreasing the dose of the current opioid analgesic, or opioid rotation (safely switching the patient to a different opioid moiety) [see DOSAGE AND ADMINISTRATION (2.4); WARNINGS AND PRECAUTIONS (5.15)].

5.9 Serotonin Syndrome with Concomitant Use of Serotonergic Drugs

Cases of serotonin syndrome, a potentially life-threatening condition, have been reported during concomitant use of methadone hydrochloride tablets with serotonergic drugs. Serotonergic drugs include selective serotonin reuptake inhibitors (SSRIs), serotonin and norepinephrine reuptake inhibitors (SNRIs), tricyclic antidepressants (TCAs), triptans, 5-HT3 receptor antagonists, drugs that affect the serotonergic neurotransmitter system (e.g., mirtazapine, trazodone, tramadol), certain muscle relaxants (i.e., cyclobenzaprine, metaxalone), and drugs that impair metabolism of serotonin (including MAO inhibitors, both those intended to treat psychiatric disorders and also others, such as linezolid and intravenous methylene blue) [see DRUG INTERACTIONS (7)]. This may occur within the recommended dosage range.

Serotonin syndrome symptoms may include mental status changes (e.g., agitation, hallucinations, coma), autonomic instability (e.g., tachycardia, labile blood pressure, hyperthermia), neuromuscular aberrations (e.g., hyperreflexia, incoordination, rigidity), and/or gastrointestinal symptoms (e.g., nausea, vomiting, diarrhea). The onset of symptoms generally occurs within several hours to a few days of concomitant use, but may occur later than that. Discontinue methadone hydrochloride tablets if serotonin syndrome is suspected.

5.10 Life-Threatening Respiratory Depression in Patients with Chronic Pulmonary Disease or in Elderly, Cachectic, or Debilitated Patients

The use of methadone hydrochloride tablets in patients with acute or severe bronchial asthma in an unmonitored setting or in the absence of resuscitative equipment is contraindicated.

Patients with Chronic Pulmonary Disease

Methadone hydrochloride tablet-treated patients with significant chronic obstructive pulmonary disease or cor pulmonale, and those with a substantially decreased respiratory reserve, hypoxia, hypercapnia, or pre-existing respiratory depression are at increased risk of decreased respiratory drive including apnea, even at recommended dosages of methadone hydrochloride tablets [see WARNINGS AND PRECAUTIONS (5.2)].

Elderly, Cachectic, or Debilitated Patients

Life-threatening respiratory depression is more likely to occur in elderly, cachectic, or debilitated patients because they may have altered pharmacokinetics or altered clearance compared to younger, healthier patients [see WARNINGS AND PRECAUTIONS (5.2)].

Regularly evaluate patients, particularly when initiating and titrating methadone hydrochloride tablets and when methadone hydrochloride tablets are given concomitantly with other drugs that depress respiration [see WARNINGS AND PRECAUTIONS (5), DRUG INTERACTIONS (7)]. Alternatively, consider the use of non-opioid analgesics in these patients.

5.11 Adrenal Insufficiency

Cases of adrenal insufficiency have been reported with opioid use, more often following greater than one month of use. Presentation of adrenal insufficiency may include non-specific symptoms and signs including nausea, vomiting, anorexia, fatigue, weakness, dizziness, and low blood pressure. If adrenal insufficiency is suspected, confirm the diagnosis with diagnostic testing as soon as possible. If adrenal insufficiency is diagnosed, treat with physiologic replacement doses of corticosteroids. Wean the patient off of the opioid to allow adrenal function to recover and continue corticosteroid treatment until adrenal function recovers. Other opioids may be tried as some cases reported use of a different opioid without recurrence of adrenal insufficiency. The information available does not identify any particular opioids as being more likely to be associated with adrenal insufficiency.

5.12 Severe Hypotension

Methadone hydrochloride tablets may cause severe hypotension including orthostatic hypotension and syncope in ambulatory patients. There is an increased risk in patients whose ability to maintain blood pressure has already been compromised by a reduced blood volume or concurrent administration of certain CNS depressant drugs (e.g., phenothiazines or general anesthetics) [see DRUG INTERACTIONS (7)]. Regularly evaluate these patients for signs of hypotension after initiating or titrating the dosage of methadone hydrochloride tablets. In patients with circulatory shock, methadone hydrochloride tablets may cause vasodilation that can further reduce cardiac output and blood pressure. Avoid the use of methadone hydrochloride tablets in patients with circulatory shock.

5.13 Risks of Use in Patients with Increased Intracranial Pressure, Brain Tumors, Head Injury, or Impaired Consciousness

In patients who may be susceptible to the intracranial effects of CO2 retention (e.g., those with evidence of increased intracranial pressure or brain tumors) methadone hydrochloride tablets may reduce respiratory drive, and the resultant CO2 retention can further increase intracranial pressure. Monitor such patients for signs of sedation and respiratory depression, particularly when initiating therapy with methadone hydrochloride tablets.

Opioids may also obscure the clinical course in a patient with a head injury.

Avoid the use of methadone hydrochloride tablets in patients with impaired consciousness or coma.

5.14 Risks of Gastrointestinal Complications

Methadone hydrochloride tablets are contraindicated in patients with known or suspected gastrointestinal obstruction, including paralytic ileus.

The methadone in methadone hydrochloride tablets may cause spasm of the sphincter of Oddi. Opioids may cause increases in the serum amylase. Regularly evaluate patients with biliary tract disease, including acute pancreatitis, for worsening symptoms.

Cases of opioid-induced esophageal dysfunction (OIED) have been reported in patients taking opioids. The risk of OIED may increase as the dose and/or duration of opioids increases. Regularly evaluate patients for signs and symptoms of OIED (e.g., dysphagia, regurgitation, non-cardiac chest pain) and, if necessary, adjust opioid therapy as clinically appropriate [see CLINICAL PHARMACOLOGY (12.2)].

5.15 Increased Risk of Seizures in Patients with Seizure Disorders

The methadone in methadone hydrochloride tablets may increase the frequency of seizures in patients with seizure disorders, and may increase the risk of seizures in other clinical settings associated with seizures. Regularly evaluate patients with a history of seizure disorders for worsened seizure control during methadone hydrochloride tablets therapy.

5.16 Withdrawal

Do not rapidly reduce or abruptly discontinue Methadone Hydrochloride Tablets in a patient physically dependent on opioids. When discontinuing Methadone Hydrochloride Tablets in a physically dependent patient, gradually taper the dosage. Rapid tapering of methadone in a patient physically dependent on opioids may lead to a withdrawal syndrome and return of pain [see DOSAGE AND ADMINISTRATION (2.6), DRUG ABUSE AND DEPENDENCE (9.3)].

Additionally, avoid the use of mixed agonist/antagonist (e.g., pentazocine, nalbuphine, and butorphanol) or partial agonist (e.g., buprenorphine) analgesics in patients who are receiving a full opioid agonist, including Methadone Hydrochloride Tablets. In these patients, mixed agonists/antagonist and partial agonist analgesics may reduce the analgesic effect and/or may precipitate withdrawal symptoms [see DRUG INTERACTIONS (7)].

5.17 Risks of Driving and Operating Machinery

Methadone hydrochloride tablets may impair the mental or physical abilities needed to perform potentially hazardous activities such as driving a car or operating machinery. Warn patients not to drive or operate dangerous machinery unless they are tolerant to the effects of methadone hydrochloride tablets and know how they will react to the medication [see PATIENT COUNSELING INFORMATION (17)].

5.18 Hypoglycemia

Cases of methadone-associated hypoglycemia have been reported, some resulting in hospitalization. In many cases, patients had predisposing risk factors (e.g., diabetes). The relationship between methadone and hypoglycemia is not fully understood but may be dose dependent. If hypoglycemia is suspected, monitor blood glucose levels, and manage the patient as clinically appropriate.

5.19 Laboratory Test Interactions

False positive urine drug screens for methadone have been reported for several drugs including diphenhydramine, doxylamine, clomipramine, chlorpromazine, thioridazine, quetiapine, and verapamil.

6 ADVERSE REACTIONS

The following serious adverse reactions are described, or described in greater detail, in other sections:

- Addiction, Abuse, and Misuse [see WARNINGS AND PRECAUTIONS (5.1)]
- Life Threatening Respiratory Depression [see WARNINGS AND PRECAUTIONS (5.2)]
- QT Prolongation [see WARNINGS AND PRECAUTIONS (5.4)]
- Neonatal Opioid Withdrawal Syndrome [see WARNINGS AND PRECAUTIONS (5.5)]
- Interactions with Benzodiazepines and other CNS Depressants [see WARNINGS AND PRECAUTIONS (5.3)]
- Opioid-Induced Hyperalgesia and Allodynia [see WARNINGS AND PRECAUTIONS (5.8)]
- Serotonin Syndrome [see WARNINGS AND PRECAUTIONS (5.9)]
- Adrenal Insufficiency [see WARNINGS AND PRECAUTIONS (5.11)]
- Severe Hypotension [see WARNINGS AND PRECAUTIONS (5.12)]
- Gastrointestinal Adverse Reactions [see WARNINGS AND PRECAUTIONS (5.14)]
- Seizures [see WARNINGS AND PRECAUTIONS (5.15)]
- Withdrawal [see WARNINGS AND PRECAUTIONS (5.16)]

The following adverse reactions associated with the use of methadone were identified in clinical studies or postmarketing reports. Because some of these reactions were reported voluntarily from a population of uncertain size, it is not always possible to reliably estimate their frequency or establish a causal relationship to drug exposure.

The major hazards of methadone are respiratory depression and, to a lesser degree, systemic hypotension. Respiratory arrest, shock, cardiac arrest, and death have occurred.

The most frequently observed adverse reactions include lightheadedness, dizziness, sedation, nausea, vomiting, and sweating. These effects seem to be more prominent in ambulatory patients and in those who are not suffering severe pain. In such individuals, lower doses are advisable.

Other adverse reactions include the following:

Body as a Whole: asthenia (weakness), edema, headache

Cardiovascular: arrhythmias, bigeminal rhythms, bradycardia, cardiomyopathy, ECG abnormalities, extrasystoles, flushing, heart failure, hypotension, palpitations, phlebitis, QT interval prolongation, syncope, T-wave inversion, tachycardia, torsades de pointes, ventricular fibrillation, ventricular tachycardia

Central Nervous System: agitation, confusion, disorientation, dysphoria, euphoria, insomnia, hallucinations, seizures, visual disturbances, congenital oculomotor disorders (nystagmus, strabismus)

Endocrine: hypogonadism, decreased testosterone

Gastrointestinal: abdominal pain, anorexia, biliary tract spasm, constipation, dry mouth, glossitis

Hematologic: reversible thrombocytopenia has been described in opioid addicts with chronic hepatitis

Metabolic: hypoglycemia, hypokalemia, hypomagnesemia, weight gain

Renal: antidiuretic effect, urinary retention or hesitancy

Reproductive: amenorrhea, reduced libido and/or potency, reduced ejaculate volume, reduced seminal vesicle and prostate secretions, decreased sperm motility, abnormalities in sperm morphology

Respiratory: pulmonary edema, respiratory depression

Skin and Subcutaneous Tissue: pruritus, urticaria, other skin rashes, and rarely, hemorrhagic urticaria

Hypersensitivity: Anaphylaxis has been reported with ingredients contained in methadone hydrochloride tablets.

Serotonin Syndrome: Cases of serotonin syndrome, a potentially life-threatening condition, have been reported during concomitant use of opioids with serotonergic drugs.

Adrenal Insufficiency: Cases of adrenal insufficiency have been reported with opioid use, more often following greater than one month of use.

Androgen Deficiency: Cases of androgen deficiency have occurred with use of opioids for an extended period of time [see CLINICAL PHARMACOLOGY (12.2)].

Hyperalgesia and Allodynia: Cases of hyperalgesia and allodynia have been reported with opioid therapy of any duration [see WARNINGS AND PRECAUTIONS (5.8)].

Hypoglycemia: Cases of hypoglycemia have been reported in patients taking methadone [see WARNINGS AND PRECAUTIONS (5.18)].

Opioid-induced esophageal dysfunction (OIED): Cases of OIED have been reported in patients taking opioids, and may occur more frequently in patients taking higher doses of opioids and/or in patients taking opioids longer term [see WARNINGS AND PRECAUTIONS (5.14)].

Adverse Reactions from Observational Studies

A prospective, observational cohort study estimated the risks of addiction, abuse, and misuse in patients initiating long-term use of Schedule II opioid analgesics between 2017 and 2021. Study participants included in one or more analyses had been enrolled in selected insurance plans or health systems for at least one year, were free of at least one outcome at baseline, completed a minimum number of follow-up assessments, and either: 1) filled multiple extended-release/long-acting opioid analgesic prescriptions during a 90-day period (n=978); or 2) filled any Schedule II opioid analgesic prescriptions covering at least 70 of 90 days (n=1,244). Those included also had no dispensing of the qualifying opioids in the previous 6 months.

Over 12 months:

• approximately 1% to 6% of participants across the two cohorts newly met criteria for addiction, as assessed with two validated interview-based measures of moderate-to-severe opioid use disorder based on Diagnostic and Statistical Manual of Mental Disorders, Fifth Edition (DSM-5) criteria, and
• approximately 9% and 22% of participants across the two cohorts newly met criteria for prescription opioid abuse and misuse [defined in DRUG ABUSE AND DEPENDENCE (9.2)], respectively, as measured with a validated self-reported instrument.

A retrospective, observational cohort study estimated the risk of opioid-involved overdose or opioid overdose-related death in patients with new long-term use of Schedule II opioid analgesics from 2006 through 2016 (n=220,249). Included patients had been enrolled in either one of the two commercial insurance programs, one managed care program, or one Medicaid program for at least 9 months. New long-term use was defined as having Schedule II opioid analgesic prescriptions covering at least 70 days’ supply over the 3 months prior to study entry and none during the preceding 6 months. Patients were excluded if they had an opioid-involved overdose in the 9 months prior to study entry. Overdose was measured using a validated medical code-based algorithm with linkage to the National Death Index database. The 5-year cumulative incidence estimates for opioid-involved overdose or opioid overdose-related death ranged from approximately 1.5% to 4% across study sites, counting only the first event during follow-up. Approximately 17% of first opioid overdoses observed over the entire study period (5-11 years, depending on the study site) were fatal. Higher baseline opioid dose was the strongest and most consistent predictor of opioid-involved overdose or opioid overdose-related death. Study exclusion criteria may have selected patients at lower risk of overdose, and substantial loss to follow-up (approximately 80%) also may have biased estimates.

The risk estimates from the studies described above may not be generalizable to all patients receiving opioid analgesics, such as those with exposures shorter or longer than the duration evaluated in the studies.

7 DRUG INTERACTIONS

Inhibitors of CYP3A4, CYP2B6, CYP2C19, CYP2C9, or CYP2D6
Clinical Impact: | Methadone undergoes hepatic N-demethylation by several cytochrome P450 (CYP) isoforms, including CYP3A4, CYP2B6, CYP2C19, CYP2C9, and CYP2D6. The concomitant use of methadone hydrochloride tablets and CYP3A4, CYP2B6, CYP2C19, CYP2C9, or CYP2D6 inhibitors can increase the plasma concentration of methadone, resulting in increased or prolonged opioid effects, and may result in a fatal overdose, particularly when an inhibitor is added after a stable dose of methadone hydrochloride tablets is achieved. These effects may be more pronounced with concomitant use of drugs that inhibit more than one of the CYP enzymes listed above.; After stopping a CYP3A4, CYP2B6, CYP2C19, CYP2C9, or CYP2D6 inhibitor, as the effects of the inhibitor decline, the methadone plasma concentration can decrease [see CLINICAL PHARMACOLOGY (12.3)], resulting in decreased opioid efficacy or withdrawal symptoms in patients physically dependent on methadone.
Intervention: | If concomitant use is necessary, consider dosage reduction of methadone hydrochloride tablets until stable drug effects are achieved. Evaluate patients at frequent intervals for respiratory depression and sedation.; If a CYP3A4, CYP2B6, CYP2C19, CYP2C9, or CYP2D6 inhibitor is discontinued, consider increasing the methadone hydrochloride tablets dosage until stable drug effects are achieved. Evaluate for signs of opioid withdrawal.
Examples: | Macrolide antibiotics (e.g., erythromycin), azole-antifungal agents (e.g. ketoconazole), protease inhibitors (e.g., ritonavir), fluconazole, fluvoxamine, some selective serotonin reuptake inhibitors (SSRIs) (e.g., sertraline, fluvoxamine)
Inducers of CYP3A4, CYP2B6, CYP2C19, or CYP2C9
Clinical Impact: | The concomitant use of methadone hydrochloride tablets and CYP3A4, CYP2B6, CYP2C19, or CYP2C9 inducers can decrease the plasma concentration of methadone [see CLINICAL PHARMACOLOGY (12.3)], resulting in decreased efficacy or onset of withdrawal symptoms in patients physically dependent on methadone. These effects could be more pronounced with concomitant use of drugs that can induce multiple CYP enzymes.; After stopping a CYP3A4, CYP2B6, CYP2C19, or CYP2C9 inducer, as the effects of the inducer decline, the methadone plasma concentration can increase [see CLINICAL PHARMACOLOGY (12.3)], which could increase or prolong both the therapeutic effects and adverse reactions, and may cause serious respiratory depression, sedation, or death.
Intervention: | If concomitant use is necessary, consider increasing the methadone hydrochloride tablets dosage until stable drug effects are achieved. Evaluate for signs of opioid withdrawal. If a CYP3A4, CYP2B6, CYP2C19, or CYP2C9 inducer is discontinued, consider methadone hydrochloride tablets dosage reduction and evaluate patients at frequent intervals for signs of respiratory depression and sedation.
Examples: | Rifampin, carbamazepine, phenytoin, St. John’s Wort, Phenobarbital
Benzodiazepines and other Central Nervous System (CNS) Depressants
Clinical Impact: | Due to additive pharmacologic effect, the concomitant use of benzodiazepines or other CNS depressants including alcohol, can increase the risk of hypotension, respiratory depression, profound sedation, coma, and death.
Intervention: | For Patients Being Treated for Pain:; Reserve concomitant prescribing of these drugs for use in patients for whom alternative treatment options are inadequate. Limit dosages and durations to the minimum required. Inform patients and caregivers of this potential interaction, educate them on the signs and symptoms of respiratory depression (including sedation). If concomitant use is warranted, consider recommending or prescribing an opioid overdose reversal agent.; For Patients Being Treated for Opioid Addiction:; Cessation of benzodiazepines or other CNS depressants is preferred in most cases of concomitant use. In some cases, monitoring in a higher level of care for taper may be appropriate. In others, gradually tapering a patient off of a prescribed benzodiazepine or other CNS depressant or decreasing to the lowest effective dose may be appropriate.; Before co-prescribing benzodiazepines for anxiety or insomnia, ensure that patients are appropriately diagnosed and consider alternative medications and non-pharmacologic treatments.; If concomitant use is warranted, strongly consider recommending or prescribing an opioid overdose reversal agent, as is recommended for all patients in treatment for opioid use disorder [see WARNINGS AND PRECAUTIONS (5.1, 5.2, 5.3)].
Examples: | Benzodiazepines and other sedatives/hypnotics, anxiolytics, tranquilizers, muscle relaxants, general anesthetics, antipsychotics, gabapentinoids (gabapentin or pregabalin), other opioids, alcohol.
Potentially Arrhythmogenic Agents
Clinical Impact: | Pharmacodynamic interactions may occur with concomitant use of methadone and potentially arrhythmogenic agents or drugs capable of inducing electrolyte disturbances (hypomagnesemia, hypokalemia).
Intervention: | Evaluate patients closely for cardiac conduction changes.
Examples: | Drugs known to have potential to prolong QT interval: Class I and III antiarrhythmics, some neuroleptics and tricyclic antidepressants, and calcium channel blockers. Drugs capable of inducing electrolyte disturbances: Diuretics, laxatives, and, in rare cases, mineralocortocoid hormones.
Serotonergic Drugs
Clinical Impact: | The concomitant use of opioids with other drugs that affect the serotonergic neurotransmitter system has resulted in serotonin syndrome [see WARNINGS AND PRECAUTIONS (5.9)].
Intervention: | If concomitant use is warranted, frequently evaluate the patient, particularly during treatment initiation and dose adjustment. Discontinue methadone hydrochloride tablets if serotonin syndrome is suspected.
Examples: | Selective serotonin reuptake inhibitors (SSRIs), serotonin and norepinephrine reuptake inhibitors (SNRIs), tricyclic antidepressants (TCAs), triptans, 5-HT3 receptor antagonists, drugs that effect the serotonin neurotransmitter system (e.g., mirtazapine, trazodone, tramadol), certain muscle relaxants (i.e., cyclobenzaprine, metaxalone), monoamine oxidase (MAO) inhibitors (those intended to treat psychiatric disorders and also others, such as linezolid and intravenous methylene blue).
Monoamine Oxidase Inhibitors (MAOIs)
Clinical Impact: | MAOI interactions with opioids may manifest as serotonin syndrome [see WARNINGS AND PRECAUTIONS (5.9)] or opioid toxicity (e.g., respiratory depression, coma) [see WARNINGS AND PRECAUTIONS (5.2)].
Intervention: | The use of methadone hydrochloride tablets is not recommended for patients taking MAOIs or within 14 days of stopping such treatment.
Mixed Agonist/Antagonist and Partial Agonist Opioid Analgesics
Clinical Impact: | May reduce the analgesic effect of methadone hydrochloride tablets and/or precipitate withdrawal symptoms.
Intervention: | Avoid concomitant use.
Examples: | Butorphanol, nalbuphine, pentazocine, buprenorphine
Muscle Relaxants
Clinical Impact: | Methadone may enhance the neuromuscular blocking action of skeletal muscle relaxants and produce an increased degree of respiratory depression.
Intervention: | Because respiratory depression may be greater than otherwise expected, decrease the dosage of methadone hydrochloride tablets and/or the muscle relaxant as necessary. Due to the risk of respiratory depression with concomitant use of skeletal muscle relaxants and opioids, consider recommending or prescribing an opioid overdose reversal agent.
Examples: | Cyclobenzaprine, metaxalone.
Diuretics
Clinical Impact: | Opioids can reduce the efficacy of diuretics by inducing the release of antidiuretic hormone.
Intervention: | Evaluate patients for signs of diminished diuresis and/or effects on blood pressure and increase the dosage of the diuretic as needed.
Anticholinergic Drugs
Clinical Impact: | The concomitant use of anticholinergic drugs may increase risk of urinary retention and/or severe constipation, which may lead to paralytic ileus.
Intervention: | Evaluate patients for signs of urinary retention or reduced gastric motility when methadone hydrochloride tablets are used concomitantly with anticholinergic drugs.

Paradoxical Effects of Antiretroviral Agents on Methadone Hydrochloride Tablets

Concurrent use of certain antiretroviral agents with CYP3A4 inhibitory activity, alone and in combination, such as abacavir, amprenavir, darunavir+ritonavir, efavirenz, nelfinavir, nevirapine, ritonavir, telaprevir, lopinavir+ritonavir, saquinavir+ritonavir, and tipranavir+ritonavir, has resulted in increased clearance or decreased plasma levels of methadone. This may result in reduced efficacy of methadone hydrochloride tablets and could precipitate a withdrawal syndrome. Evaluate methadone-maintained patients receiving any of these anti-retroviral therapies closely for evidence of withdrawal effects and adjust the methadone dose accordingly.

Effects of Methadone Hydrochloride Tablets on Antiretroviral Agents

Didanosine and Stavudine:Experimental evidence demonstrated that methadone decreased the area under the concentration-time curve (AUC) and peak levels for didanosine and stavudine, with a more significant decrease for didanosine. Methadone disposition was not substantially altered.

Zidovudine: Experimental evidence demonstrated that methadone increased the AUC of zidovudine, which could result in toxic effects.

Effects of Methadone Hydrochloride Tablets on Antidepressants

Desipramine: Blood levels of desipramine have increased with concurrent methadone administration.

8 USE IN SPECIFIC POPULATIONS

8.1 Pregnancy

Risk Summary

The majority of available data from clinical trials, observational studies, case series, and case reports on methadone use in pregnancy do not indicate an increased risk of major malformations specifically due to methadone.

Pregnant women involved in methadone maintenance programs have been reported to have improved prenatal care leading to reduced incidence of obstetric and fetal complications and neonatal morbidity and mortality when compared to women using illicit drugs. Several factors, including maternal use of illicit drugs, nutrition, infection and psychosocial circumstances, complicate the interpretation of investigations of the children of women who take methadone during pregnancy. Information is limited regarding dose and duration of methadone use during pregnancy, and most maternal exposure in these studies appears to occur after the first trimester of pregnancy (see Data).

Neonatal opioid withdrawal syndrome (NOWS) is an expected and treatable outcome of use of opioids for an extended period of time during pregnancy [see WARNINGS AND PRECAUTIONS (5.6)].

In published animal reproduction studies, methadone administered subcutaneously during the early gestational period produced neural tube defects (i.e., exencephaly and cranioschisis) in the hamster at doses 2 times the human daily oral dose of 120 mg/day on a mg/m^2 basis (HDD) and in mice at doses equivalent to the HDD. Administration of methadone to pregnant animals during organogenesis and through lactation resulted decreased litter size, increased pup mortality, decreased pup body weights, developmental delays, and long-term neurochemical changes in the brain of offspring which correlate with altered behavioral responses that persist through adulthood at exposures comparable to and less than the HDD. Administration of methadone to male rodents prior to mating with untreated females resulted in increased neonatal mortality and significant differences in behavioral tests in the offspring at exposures comparable to and less than the HDD [see Data]. Based on animal data, advise pregnant women of the potential risk to a fetus.

The estimated background risk of major birth defects and miscarriage for the indicated population is unknown. All pregnancies have a background risk of birth defect, loss, or other adverse outcomes. In the U.S. general population, the estimated background risk of major birth defects and miscarriage in clinically recognized pregnancies is 2 to 4% and 15 to 20%, respectively.

Clinical Considerations

Disease-Associated Maternal and Embryo-Fetal Risk: Untreated opioid addiction in pregnancy is associated with adverse obstetrical outcomes such as low birth weight, preterm birth, and fetal death. In addition, untreated opioid addiction often results in continued or relapsing illicit opioid use.

Dosage Adjustment During Pregnancy: Dosage adjustment using higher doses or administering the daily dose in divided doses may be necessary in pregnant women treated with methadone hydrochloride tablets. Pregnant women appear to have significantly lower trough plasma methadone concentrations, increased plasma methadone clearance, and shorter methadone half-life than after delivery [see DOSAGE AND ADMINISTRATION (2.9) and Clinical Pharmacology (12.3)]. Withdrawal signs and symptoms should be closely monitored and the dose adjusted as necessary.

Fetal/Neonatal Adverse Reactions: Neonatal opioid withdrawal syndrome may occur in newborn infants of mothers who are receiving treatment with methadone hydrochloride tablets.

Neonatal opioid withdrawal syndrome presents as irritability, hyperactivity and abnormal sleep pattern, high pitched cry, tremor, vomiting, diarrhea, and/or failure to gain weight. Signs of neonatal withdrawal usually occur in the first days after birth. The duration and severity of neonatal opioid withdrawal syndrome may vary. Observe newborns for signs of neonatal opioid withdrawal syndrome and manage accordingly [see WARNINGS AND PRECAUTIONS (5.5)].

Labor or Delivery: Opioid-dependent women on methadone maintenance therapy may require additional analgesia during labor.

Monitor neonates exposed to opioid analgesics during labor for signs of excess sedation and respiratory depression.

Data

Human Data: The majority of available data from clinical trials, observational studies, case series, and case reports on methadone use in pregnancy do not indicate an increased risk of major malformations specifically due to methadone. Findings regarding specific major malformations, decreased fetal growth, premature birth and Sudden Infant Death Syndrome have been inconsistent. Children prenatally exposed to methadone have been reported to demonstrate mild but persistent deficits in performance on psychometric and behavioral tests and visual abnormalities.

In a multicenter, double-blind, randomized, controlled trial [Maternal Opioid Treatment: Human Experimental Research (MOTHER)] designed primarily to assess neonatal opioid withdrawal effects, opioid-dependent pregnant women were randomized to buprenorphine (n=86) or methadone (n=89) treatment, with enrollment at an average gestational age of 18.7 weeks in both groups. A total of 28 of the 86 women in the buprenorphine group (33%) and 16 of the 89 women in the methadone group (18%) discontinued treatment before the end of pregnancy.

Among women who remained in treatment until delivery, there was no difference between methadone-treated and buprenorphine-treated groups in the number of neonates requiring NOWS treatment or in the peak severity of NOWS. Buprenorphine-exposed neonates required less morphine (mean total dose, 1.1 mg vs 10.4 mg), had shorter hospital stays (10.0 days vs. 17.5 days), and shorter duration of treatment for NOWS (4.1 days vs. 9.9 days) compared to the methadone-exposed group. There were no differences between groups in other primary outcomes (neonatal head circumference) or secondary outcomes (weight and length at birth, preterm birth, gestational age at delivery, and 1-minute and 5-minute Apgar scores), or in the rates of maternal or neonatal adverse events. The outcomes among mothers who discontinued treatment before delivery and may have relapsed to illicit opioid use are not known. Because of the imbalance in discontinuation rates between the methadone and buprenorphine groups, the study findings are difficult to interpret.

Animal Data: Formal reproductive and developmental toxicology studies for methadone have not been conducted. Exposure margins for the following published study reports are based on a human daily dose (HDD) of 120 mg methadone using a body surface area comparison.

In a published study in pregnant hamsters, a single subcutaneous dose of methadone ranging from 31 mg/kg (2 times the HDD) to 185 mg/kg on Gestation Day 8 resulted in a decrease in the number of fetuses per litter and an increase in the percentage of fetuses exhibiting neural tube defects including exencephaly, cranioschisis, and “various other lesions.” The majority of the doses tested also resulted in maternal death. In a study in pregnant JBT/Jd mice, a single subcutaneous dose of 22 to 24 mg/kg methadone (approximately equivalent to the HDD) administered on Gestation Day 9 produced exencephaly in 11% of the embryos. In another study in pregnant mice, subcutaneous doses up to 28 mg/kg/day methadone (equivalent to the HDD) administered from Gestation Day 6 to 15 resulted in no malformations, but there were increased post-implantation loss and decreased live fetuses at 10 mg/kg/day or greater (0.4 times the HDD) and decreased ossification and fetal body weight at 20 mg/kg/day or greater (0.8 times the HDD). In a second study of pregnant mice dosed with subcutaneous doses up to 28 mg/kg/day methadone from Gestation Day 6 to 15, there was decreased pup viability, delayed onset of development of negative phototaxis and eye opening, increased righting reflexes at 5 mg/kg/day or greater (0.2 times the HDD), and decreased number of live pups at birth and decreased pup weight gain at 20 mg/kg/day or greater (0.8 times the HDD).

No effects were reported in a study of pregnant rats and rabbits at oral doses up to 40 mg/kg (3 and 6 times, respectively, the HDD) administered from Gestation Days 6 to 15 and 6 to 18, respectively.

When pregnant rats were treated with intraperitoneal doses of 2.5, 5, or 7.5 mg/kg methadone from one week prior to mating, through gestation until the end of lactation period, 5 mg/kg or greater (0.4 times the HDD) methadone resulted in decreases in litter size and live pups born and 7.5 mg/kg (0.6 times the HDD) resulted in decreased birth weights. Furthermore, decreased pup viability and pup body weight gain at 2.5 mg/kg or greater (0.2 times the HDD) were noted during the preweaning period.

Additional animal data demonstrates evidence for neurochemical changes in the brains of offspring from methadone-treated pregnant rats, including changes to the cholinergic, dopaminergic, noradrenergic and serotonergic systems at doses below the HDD. Other animal studies have reported that prenatal and/or postnatal exposure to opioids including methadone alters neuronal development and behavior in the offspring including alterations in learning ability, motor activity, thermal regulation, nociceptive responses, and sensitivity to drugs at doses below the HDD. Treatment of pregnant rats subcutaneously with 5 mg/kg methadone from Gestation Day 14 to 19 (0.4 times the HDD) reduced fetal blood testosterone and androstenedione in males.

Published animal data have reported increased neonatal mortality in the offspring of male rodents that were treated with methadone at doses comparable to and less than the HDD for 1 to 12 days before and/or during mating (with more pronounced effects in the first 4 days). In these studies, the female rodents were not treated with methadone, indicating paternally-mediated developmental toxicity. Specifically, methadone administered to the male rat prior to mating with methadone-naïve females resulted in decreased weight gain in progeny after weaning. The male progeny demonstrated reduced thymus weights, whereas the female progeny demonstrated increased adrenal weights. Behavioral testing of these male and female progeny revealed significant differences in behavioral tests compared to control animals, suggesting that paternal methadone exposure can produce physiological and behavioral changes in progeny in this model. Examination of uterine contents of methadone-naïve female mice bred to methadone-treated male mice (once a day for three consecutive days) indicated that methadone treatment produced an increase in the rate of preimplantation deaths in all post-meiotic states at 1 mg/kg/day or greater (0.04 times the HDD). Chromosome analysis revealed a dose-dependent increase in the frequency of chromosomal abnormalities at 1 mg/kg/day or greater.

Studies demonstrated that methadone treatment of male rats for 21 to 32 days prior to mating with methadone-naïve females did not produce any adverse effects, suggesting that prolonged methadone treatment of the male rat resulted in tolerance to the developmental toxicities noted in the progeny. Mechanistic studies in this rat model suggest that the developmental effects of “paternal” methadone on the progeny appear to be due to decreased testosterone production. These animal data mirror the reported clinical findings of decreased testosterone levels in human males on methadone maintenance therapy for opioid addiction and in males receiving chronic intraspinal opioids.

8.2 Lactation

Risk Summary

Based on two small clinical studies, methadone was present in low levels in human milk, but the exposed infants in these studies did not show adverse reactions. Based on an average milk consumption of 150 mL/kg/day, an infant would consume approximately 17.4 mcg/kg/day which is approximately 2 to 3% of the oral maternal dose. There have been rare case reports of sedation and respiratory depression in infants exposed to methadone through breast milk (see Data). Monitor infants exposed to methadone hydrochloride tablets through breastmilk for excess sedation and respiratory depression. The developmental and health benefits of breastfeeding should be considered along with the mother’s clinical need for methadone and any potential adverse effects on the breastfed child from the drug or from the underlying maternal condition.

Data

In a study of ten breastfeeding women maintained on oral methadone doses of 10 to 80 mg/day, methadone concentrations from 50 to 570 mcg/L in milk were reported, which, in the majority of samples, were lower than maternal serum drug concentrations at steady state. Peak methadone levels in milk occur approximately 4 to 5 hours after an oral dose.

In a study of twelve breastfeeding women maintained on oral methadone doses of 20 to 80 mg/day, methadone concentrations from 39 to 232 mcg/L in milk were reported. Based on an average milk consumption of 150 mL/kg/day, an infant would consume approximately 17.4 mcg/kg/day which is approximately 2 to 3% of the oral maternal dose. Methadone has been detected in very low plasma concentrations in some infants whose mothers were taking methadone.

8.3 Females and Males of Reproductive Potential

Infertility

The effect of methadone hydrochloride tablets on fertility is unknown. Use of opioids for an extended period of time may cause reduced fertility in females and males of reproductive potential It is not known whether these effects on fertility are reversible [see ADVERSE REACTIONS (6), CLINICAL PHARMACOLOGY (12.2), NONCLINICAL PHARMACOLOGY (13.1)]. Reproductive function in human males may be decreased by methadone treatment. Reductions in ejaculate volume and seminal vesicle and prostate secretions have been reported in methadone-treated individuals. In addition, reductions in serum testosterone levels and sperm motility, and abnormalities in sperm morphology have been reported.

In published animal studies, methadone produces a significant regression of sex accessory organs and testes of male mice and rats and administration of methadone to pregnant rats reduced fetal blood testosterone and androstenedione in male offspring [see NONCLINICAL TOXICOLOGY (13)].

8.4 Pediatric Use

The safety, effectiveness, and pharmacokinetics of methadone in pediatric patients below the age of 18 years have not been established.

8.5 Geriatric Use

Clinical studies of methadone did not include sufficient numbers of subjects aged 65 and over to determine whether they respond differently compared to younger subjects. Other reported clinical experience has not identified differences in responses between elderly and younger patients.

Elderly patients (aged 65 years or older) may have increased sensitivity to methadone. In general, use caution when selecting a dosage for an elderly patient, usually starting at the low end of the dosing range, reflecting the greater frequency of decreased hepatic, renal, or cardiac function and of concomitant disease or other drug therapy.

Respiratory depression is the chief risk for elderly patients treated with opioids, and has occurred after large initial doses were administered to patients who were not opioid-tolerant or when opioids were co-administered with other agents that depress respiration. Titrate the dosage of methadone hydrochloride tablets slowly in geriatric patients and frequently reevaluate the patient for signs of central nervous system and respiratory depression [see WARNINGS AND PRECAUTIONS (5.10)].

Methadone is known to be substantially excreted by the kidney, and the risk of adverse reactions to this drug may be greater in patients with impaired renal function. Because elderly patients are more likely to have decreased renal function, care should be taken in dose selection, and it may be useful to regularly evaluate renal function.

8.6 Hepatic Impairment

Methadone pharmacokinetics have not been extensively evaluated in patients with hepatic insufficiency. Methadone is metabolized by hepatic pathways; therefore, patients with liver impairment may be at risk of increased systemic exposure to methadone after multiple dosing. Start these patients on lower doses and titrate slowly while carefully monitoring for signs of respiratory and central nervous system depression.

8.7 Renal Impairment

Methadone pharmacokinetics have not been extensively evaluated in patients with renal insufficiency. Since unmetabolized methadone and its metabolites are excreted in urine to a variable degree, start these patients on lower doses and with longer dosing intervals and titrate slowly while carefully monitoring for signs of respiratory and central nervous system depression.

9 DRUG ABUSE AND DEPENDENCE

9.1 Controlled Substance

Methadone hydrochloride tablets contain methadone, a Schedule II controlled substance.

9.2 Abuse

Methadone hydrochloride tablets contains methadone, a substance with high potential for misuse and abuse, which can lead to the development of substance use disorder, including addiction [see WARNINGS AND PRECAUTIONS (5.1)].

Misuse is the intentional use, for therapeutic purposes, of a drug by an individual in a way other than prescribed by a healthcare provider or for whom it was not prescribed.

Abuse is the intentional, non-therapeutic use of a drug, even once, for its desirable psychological or physiological effects.

Drug addiction is a cluster of behavioral, cognitive, and physiological phenomena that may include a strong desire to take the drug, difficulties in controlling drug use (e.g., continuing drug use despite harmful consequences, giving a higher priority to drug use than other activities and obligations), and possible tolerance or physical dependence.

Misuse and abuse of methadone hydrochloride tablets increases risk of overdose, which may lead to central nervous system and respiratory depression, hypotension, seizures, and death. The risk is increased with concurrent abuse of methadone hydrochloride tablets with alcohol and other CNS depressants. Abuse of and addiction to opioids in some individuals may not be accompanied by concurrent tolerance and symptoms of physical dependence. In addition, abuse of opioids can occur in the absence of addiction.

All patients treated with opioids require careful and frequent reevaluation for signs of misuse, abuse, and addiction, because use of opioid analgesic products carries the risk of addiction even under appropriate medical use. Patients at high risk of methadone hydrochloride tablets abuse include those with a history of prolonged use of any opioid, including products containing methadone, those with a history of drug or alcohol abuse, or those who use methadone hydrochloride tablets in combination with other abused drugs.

“Drug-seeking” behavior is very common in persons with substance use disorders. Drug-seeking tactics include emergency calls or visits near the end of office hours, refusal to undergo appropriate examination, testing, or referral, repeated “loss” of prescriptions, tampering with prescriptions, and reluctance to provide prior medical records or contact information for other treating healthcare provider(s). “Doctor shopping” (visiting multiple prescribers to obtain additional prescriptions) is common among people who abuse drugs and people with substance use disorder. Preoccupation with achieving adequate pain relief can be appropriate behavior in a patient with inadequate pain control.

Methadone hydrochloride tablets, like other opioids, can be diverted for nonmedical use into illicit channels of distribution. Careful record-keeping of prescribing information, including quantity, frequency, and renewal requests, as required by state and federal law, is strongly advised.

Proper assessment of the patient, proper prescribing practices, periodic reevaluation of therapy, and proper dispensing and storage are appropriate measures that help to limit abuse of opioid drugs.

Risks Specific to Abuse of Methadone Hydrochloride Tablets

Abuse of methadone hydrochloride tablets poses a risk of overdose and death. The risk is increased with concurrent use of methadone hydrochloride tablets with alcohol and/or other CNS depressants.

Methadone hydrochloride tablets are approved for oral use only. Inappropriate intravenous, intramuscular, or subcutaneous use of methadone hydrochloride tablets can result in death, local tissue necrosis, infection, pulmonary granulomas, increased risk of endocarditis, and valvular heart injury, and embolism.

Parenteral drug abuse is commonly associated with transmission of infectious diseases such as hepatitis and HIV.

9.3 Dependence

Both tolerance and physical dependence can develop during chronic opioid therapy.

Tolerance is a physiological state characterized by a reduced response to a drug after repeated administration (i.e., a higher dose of a drug is required to produce the same effect that was once obtained at a lower dose).

Physical dependence is a state that develops as a result of a physiological adaptation in response to repeated drug use, manifested by withdrawal signs and symptoms after abrupt discontinuation or a significant dose reduction of a drug.

Withdrawal is also precipitated through the administration of drugs with opioid antagonist activity (e.g., naloxone, nalmefene), mixed agonist/ antagonist analgesics (e.g., pentazocine, butorphanol, nalbuphine), or partial agonists (e.g., buprenorphine). Physical dependence may not occur to a clinically significant degree until after several days to weeks of continued use.

Do not rapidly reduce or abruptly discontinue methadone hydrochloride tablets in a patient physically dependent on opioids. Rapid tapering of methadone hydrochloride tablets in a patient physically dependent on opioids may lead to serious withdrawal symptoms, uncontrolled pain, and suicide. Rapid discontinuation has also been associated with attempts to find other sources of opioid analgesics, which may be confused with drug-seeking for abuse.

When discontinuing methadone hydrochloride tablets, gradually taper the dosage using a patient-specific plan that considers the following: the dose of methadone hydrochloride tablets the patient has been taking, the duration of treatment, and the physical and psychological attributes of the patient. To improve the likelihood of a successful taper and minimize withdrawal symptoms, it is important that the opioid tapering schedule is agreed upon by the patient. In patients taking opioids for an extended period of time at high doses, ensure that a multimodal approach to pain management, including mental health support (if needed), is in place prior to initiating an opioid analgesic taper [see DOSAGE AND ADMINISTRATION (2.6), AND WARNINGS AND PRECAUTIONS (5.16)].

Infants born to mothers physically dependent on opioids will also be physically dependent and may exhibit respiratory difficulties and withdrawal signs [see USE IN SPECIFIC POPULATIONS (8.1)].

10 OVERDOSAGE

Clinical Presentation

Acute overdosage with methadone can be manifested by respiratory depression, somnolence progressing to stupor or coma, skeletal-muscle flaccidity, cold and clammy skin, constricted pupils, and, in some cases, pulmonary edema, bradycardia, hypotension, hypoglycemia, partial or complete airway obstruction, atypical snoring, and death. Marked mydriasis rather than miosis may be seen with hypoxia in overdose situations [see CLINICAL PHARMACOLOGY (12.2)].In severe overdosage, particularly by the intravenous route, apnea, circulatory collapse, cardiac arrest, and death may occur.

Methadone overdosage is associated with rhabdomyolsis. Seek medical attention, especially if abuse/misuse results in prolonged immobilization. Toxic leukoencephalopathy has been reported after opioid overdose, and can present hours, days, or weeks after apparent recovery from the initial intoxication. Hearing loss has been reported after methadone overdose, in some cases permanent.

Treatment of Overdose

In case of overdose, priorities are the reestablishment of a patent and protected airway and institution of assisted or controlled ventilation, if needed. Employ other supportive measures (including oxygen and vasopressors) in the management of circulatory shock and pulmonary edema as indicated. Cardiac arrest or arrhythmias will require advanced life-support measures.

For clinically significant respiratory or circulatory depression secondary to opioid overdose, administer an opioid overdose reversal agent such as naloxone or nalmefene.

Because the duration of reversal would be expected to be less than the duration of action of methadone in methadone hydrochloride tablets, carefully monitor the patient until spontaneous respiration is reliably reestablished. If the response to opioid reversal agent is suboptimal or not sustained, administer additional reversal agent as directed in the product’s prescribing information.

In an individual physically dependent on opioids, administration of the recommended usual dosage of the overdose reversal agent will precipitate an acute withdrawal syndrome. The severity of the withdrawal symptoms experienced will depend on the degree of physical dependence and the dose of the reversal agent administered. If a decision is made to treat serious respiratory depression in the physically dependent patient, administration of the opioid overdose reversal agent should be begun with care and by titration with smaller than usual doses of the reversal agent.

11 DESCRIPTION

Methadone hydrochloride is chemically described as 6-(dimethylamino)-4,4-diphenyl-3-hepatanone hydrochloride. Methadone hydrochloride USP is a white powder. Its molecular formula is C21H27NO• HCl and it has a molecular weight of 345.91. Methadone hydrochloride has a melting point of 235°C, and a pKa of 8.25 in water at 20°C. Its octanol/water partition coefficient at pH 7.4 is 117. A solution (1:100) in water has a pH between 4.5 and 6.5.

It has the following structural formula:

Methadone hydrochloride tablets are available for oral administration containing 10 mg of methadone hydrochloride USP. Each tablet contains following inactive ingredients: magnesium stearate, microcrystalline cellulose, and pregelatinized starch.

12 CLINICAL PHARMACOLOGY

12.1 Mechanism of Action

Methadone hydrochloride is a mu-agonist; a synthetic opioid with multiple actions qualitatively similar to those of morphine, the most prominent of which involves the central nervous system and organs composed of smooth muscle. The principal therapeutic uses for methadone are for analgesia and for detoxification or maintenance in opioid addiction. The methadone withdrawal syndrome, although qualitatively similar to that of morphine, differs in that the onset is slower, the course is more prolonged, and the symptoms are less severe.

Some data also indicate that methadone acts as an antagonist at the N-methyl-D-aspartate (NMDA) receptor. The contribution of NMDA receptor antagonism to methadone’s efficacy is unknown.

12.2 Pharmacodynamics

Effects on the Central Nervous System

Methadone produces respiratory depression by direct action on brain stem respiratory centers. The respiratory depression involves a reduction in the responsiveness of the brain stem respiratory centers to both increases in carbon dioxide tension and electrical stimulation.

Methadone causes miosis, even in total darkness. Pinpoint pupils are a sign of opioid overdose but are not pathognomonic (e.g., pontine lesions of hemorrhagic or ischemic origins may produce similar findings). Marked mydriasis rather than miosis may be seen due to hypoxia in overdose situations.

Some NMDA receptor antagonists have been shown to produce neurotoxic effects in animals.

Effects on the Gastrointestinal Tract and Other Smooth Muscle

Methadone causes a reduction in motility associated with an increase in smooth muscle tone in the antrum of the stomach and duodenum. Digestion of food in the small intestine is delayed and propulsive contractions are decreased. Propulsive peristaltic waves in the colon are decreased, while tone is increased to the point of spasm, resulting in constipation. Other opioid-induced effects may include a reduction in biliary and pancreatic secretions, spasm of sphincter of Oddi, transient elevations in serum amylase, and opioid-induced esophageal dysfunction (OIED).

Effects on the Cardiovascular System

Methadone produces peripheral vasodilation, which may result in orthostatic hypotension or syncope. Manifestations of histamine release and/or peripheral vasodilation may include pruritus, flushing, red eyes, sweating, and/or orthostatic hypotension.

Effects on the Endocrine System

Opioids inhibit the secretion of adrenocorticotropic hormone (ACTH), cortisol, and luteinizing hormone (LH) in humans [see ADVERSE REACTIONS (6)]. They also stimulate prolactin, growth hormone (GH) secretion, and pancreatic secretion of insulin and glucagon.

Use of opioids for an extended period of time may influence the hypothalamic-pituitary-gonadal axis, leading to androgen deficiency that may manifest as low libido, impotence, erectile dysfunction, amenorrhea, or infertility. The causal role of opioids in the clinical syndrome of hypogonadism is unknown because the various medical, physical, lifestyle, and psychological stressors that may influence gonadal hormone levels have not been adequately controlled for in studies conducted to date [see ADVERSE REACTIONS (6)].

Effects on the Immune System

Opioids have been shown to have a variety of effects on components of the immune system in vitro and animal models. The clinical significance of these findings is unknown. Overall, the effects of opioids appear to be modestly immunosuppressive.

Concentration–Efficacy Relationships

The minimum effective analgesic concentration will vary widely among patients, especially among patients who have been previously treated with opioid agonists. The minimum effective analgesic concentration of methadone for any individual patient may increase over time due to an increase in pain, the development of a new pain syndrome, and/or the development of analgesic tolerance [see DOSAGE AND ADMINISTRATION (2.2, 2.5)].

Concentration–Adverse Reaction Relationships

The minimum effective analgesic concentration will vary widely among patients, especially among patients who have been previously treated with extended-release agonist opioids. The In opioid-tolerant patients, the situation may be altered by the development of tolerance to opioid-related adverse reactions [see Dosage and Administration (2.2, 2.4, 2.5)].

12.3 Pharmacokinetics

Absorption

Following oral administration the bioavailability of methadone ranges between 36 to 100% and peak plasma concentrations are achieved between 1 to 7.5 hours. Dose proportionality of methadone pharmacokinetics is not known. However, after administration of daily oral doses ranging from 10 to 225 mg, the steady-state plasma concentrations ranged between 65 to 630 ng/mL and the peak concentrations ranged between 124 to 1255 ng/mL. Effect of food on the bioavailability of methadone has not been evaluated.

Distribution

Methadone is a lipophilic drug and the steady-state volume of distribution ranges between 1.0 to 8.0 L/kg. In plasma, methadone is predominantly bound to α1-acid glycoprotein (85% to 90%). Methadone is secreted in saliva, breast milk, amniotic fluid and umbilical cord plasma.

Elimination

Metabolism: Methadone is primarily metabolized by N-demethylation to an inactive metabolite, 2-ethylidene-1,5-dimethyl-3,3-diphenylpyrrolidene (EDDP). Cytochrome P450 enzymes, primarily CYP3A4, CYP2B6, CYP2C19, CYP2C9 and CYP2D6, are responsible for conversion of methadone to EDDP and other inactive metabolites, which are excreted mainly in the urine. Methadone appears to be a substrate for P-glycoprotein but its pharmacokinetics do not appear to be significantly altered in case of P-glycoprotein polymorphism or inhibition.

Excretion: The elimination of methadone is mediated by extensive biotransformation, followed by renal and fecal excretion. Published reports indicate that after multiple dose administration the apparent plasma clearance of methadone ranged between 1.4 and 126 L/h, and the terminal half-life (T1/2) was highly variable and ranged between 8 to 59 hours in different studies. Methadone is a basic (pKa=9.2) compound and the pH of the urinary tract can alter its disposition in plasma. Also, since methadone is lipophilic, it has been known to persist in the liver and other tissues. The slow release from the liver and other tissues may prolong the duration of methadone action despite low plasma concentrations.

Drug Interaction Studies

Cytochrome P450 Interactions: Methadone undergoes hepatic N-demethylation by cytochrome P450 (CYP) isoforms, principally CYP3A4, CYP2B6, CYP2C19, CYP2C9 and CYP2D6. Co-administration of methadone with CYP inducers may result in more rapid metabolism and potential for decreased effects of methadone, whereas administration with CYP inhibitors may reduce metabolism and potentiate methadone’s effects. Although antiretroviral drugs such as efavirenz, nelfinavir, nevirapine, ritonavir, lopinavir+ritonavir combination are known to inhibit some CYPs, they are shown to reduce the plasma levels of methadone, possibly due to CYP induction activity [see DRUG INTERACTIONS (7)].

Cytochrome P450 Inducers: The following drug interactions were reported following co-administration of methadone with known inducers of cytochrome P450 enzymes:

Rifampin: In patients well-stabilized on methadone, concomitant administration of rifampin resulted in a marked reduction in serum methadone levels and a concurrent appearance of withdrawal symptoms.

Phenytoin: In a pharmacokinetic study with patients on methadone maintenance therapy, phenytoin administration (250 mg twice daily initially for 1 day followed by 300 mg daily for 3 to 4 days) resulted in an approximately 50% reduction in methadone exposure and withdrawal symptoms occurred concurrently. Upon discontinuation of phenytoin, the incidence of withdrawal symptoms decreased and methadone exposure increased to a level comparable to that prior to phenytoin administration.

St. John’s Wort, Phenobarbital, Carbamazepine: Administration of methadone with other CYP3A4 inducers may result in withdrawal symptoms.

Cytochrome P450 Inhibitors:

Voriconazole: Voriconazole can inhibit the activity of CYP3A4, CYP2C9, and CYP2C19. Repeat dose administration of oral voriconazole (400 mg every 12 hours for 1 day, then 200 mg every 12 hours for 4 days) increased the peak plasma concentration (Cmax) and AUC of (R)-methadone by 31% and 47%, respectively, in subjects receiving a methadone maintenance dose (30 to 100 mg daily). The Cmax and AUC of (S)-methadone increased by 65% and 103%, respectively. Increased plasma concentrations of methadone have been associated with toxicity including QT prolongation. Frequent monitoring for adverse events and toxicity related to methadone is recommended during co-administration. Dose reduction of methadone may be needed [see DRUG INTERACTIONS (7)].

Antiretroviral Drugs: Although antiretroviral drugs such as efavirenz, nelfinavir, nevirapine, ritonavir, telaprevir, lopinavir+ritonavir combination are known to inhibit some CYPs, they are shown to reduce the plasma levels of methadone, possibly due to CYP induction activity.

Abacavir, amprenavir, darunavir+ritonavir, efavirenz, nelfinavir, nevirapine, ritonavir, telaprevir, lopinavir+ritonavir, saquinavir+ritonavir, tipranavir+ritonavir combination: Co-administration of these anti-retroviral agents resulted in increased clearance or decreased plasma levels of methadone [see DRUG INTERACTIONS (7)].

Didanosine and Stavudine: Methadone decreased the AUC and peak levels for didanosine and stavudine, with a more significant decrease for didanosine. Methadone disposition was not substantially altered [see DRUG INTERACTIONS (7)].

Zidovudine: Methadone increased the AUC of zidovudine which could result in toxic effects [see DRUG INTERACTIONS (7)].

13 NONCLINICAL TOXICOLOGY

13.1 Carcinogenesis, Mutagenesis, Impairment of Fertility

Carcinogenesis

The results of carcinogenicity assessment in B6C2F1 mice and Fischer 344 rats following dietary administration of two doses of methadone HCl have been published. Mice consumed 15 mg/kg/day or 60 mg/kg/day methadone for two years. These doses were approximately 0.6 and 2.5 times a human daily oral dose of 120 mg/day on a body surface area basis (HDD). There was a significant increase in pituitary adenomas in female mice treated with 15 mg/kg/day but not with 60 mg/kg/day. Under the conditions of the assay, there was no clear evidence for a treatment-related increase in the incidence of neoplasms in male rats. Due to decreased food consumption in males at the high dose, male rats consumed 16 mg/kg/day and 28 mg/kg/day of methadone for two years. These doses were approximately 1.3 and 2.3 times the HDD. In contrast, female rats consumed 46 mg/kg/day or 88 mg/kg/day for two years. These doses were approximately 3.7 and 7.1 times the HDD. Under the conditions of the assay, there was no clear evidence for a treatment-related increase in the incidence of neoplasms in either male or female rats.

Mutagenesis

There are several published reports on the potential genetic toxicity of methadone. Methadone tested positive in the in vivo mouse dominant lethal assay and the in vivo mammalian spermatogonial chromosome aberration test. Additionally, methadone tested positive in the E. coli DNA repair system and Neurospora crassa and mouse lymphoma forward mutation assays. In contrast, methadone tested negative in tests for chromosome breakage and disjunction and sex-linked recessive lethal gene mutations in germ cells of Drosophila using feeding and injection procedures.

Impairment of Fertility

Published animal studies show that methadone treatment of males can alter reproductive function. Methadone produces decreased sexual activity (mating) of male rats at 10 mg/kg/day (corresponding to 0.3 times the human daily oral dose of 120 mg/day based on body surface area). Methadone also produces a significant regression of sex accessory organs and testes of male mice and rats at 0.2 and 0.8 times the HDD, respectively. Methadone treatment of pregnant rats from Gestation Day 14 to 19 reduced fetal blood testosterone and androstenedione in males. Decreased serum levels of testosterone were observed in male rats that were treated with methadone (1.3 to 3.3 mg/kg/day for 14 days, corresponding to 0.1 to 0.3 times the HDD) or 10 to 15 mg/kg/day for 10 days (0.8 to 1.2 times the HDD).

16 HOW SUPPLIED/STORAGE AND HANDLING

Methadone Hydrochloride Tablets, USP

10 mg tablets are white, round, biconvex tablets, scored on one side and debossed with "N" above the score and "128" below the score and plain on the other side.

NDC 66689-836-99: Bottles of 100 Tablets

Store at 20° to 25°C (68° to 77°F), with excursions permitted between 15° to 30°C (59° to 86°F) [See USP Controlled Room Temperature.]

Store Methadone Hydrochloride Tablets securely and dispose of properly [see PATIENT COUNSELING INFORMATION (17)]

17 PATIENT COUNSELING INFORMATION

Advise the patient to read the FDA-approved patient labeling (Medication Guide)

Storage and Disposal

Because of the risks associated with accidental ingestion, misuse, and abuse, advise patients to store methadone hydrochloride tablets securely, out of sight and reach of children, and in a location not accessible by others, including visitors to the home. Inform patients that leaving methadone hydrochloride tablets unsecured can pose a deadly risk to others in the home [see WARNINGS AND PRECAUTIONS (5.1, 5.2), DRUG ABUSE AND DEPENDENCE (9.2)].

Advise patients and caregivers that when medicines are no longer needed, they should be disposed of promptly. Expired, unwanted, or unused methadone hydrochloride tablets should be disposed of by flushing the unused medication down the toilet if a drug take-back option is not readily available. Inform patients that they can visit www.fda.gov/drugdisposal for a complete list of medicines recommended for disposal by flushing, as well as additional information on disposal of unused medicines.

Addiction, Abuse, and Misuse

Inform patients that the use of methadone hydrochloride tablets, even when taken as recommended, can result in addiction, abuse, and misuse, which can lead to overdose or death [see WARNINGS AND PRECAUTIONS (5.1)]. Instruct patients not to share methadone hydrochloride tablets with others and to take steps to protect methadone hydrochloride tablets from theft or misuse.

Life-Threatening Respiratory Depression

Inform patients of the risk of life-threatening respiratory depression, including information that the risk is greatest when starting methadone hydrochloride tablets or when the dosage is increased, and that it can occur even at recommended dosages.

Educate patients and caregivers on how to recognize respiratory depression and emphasize the importance of calling 911 or getting emergency medical help right away in the event of a known or suspected overdose [see WARNINGS AND PRECAUTIONS (5.2)].

Accidental Ingestion

Inform patients that accidental ingestion, especially by children, may result in respiratory depression or death [see WARNINGS AND PRECAUTIONS (5.2)].

Symptoms of Arrhythmia

Instruct patients to seek medical attention immediately if they experience symptoms suggestive of an arrhythmia (such as palpitations, near syncope, or syncope) when taking methadone [see WARNINGS AND PRECAUTIONS (5.4)].

Interactions with Benzodiazepines and Other CNS Depressants

Inform patients and caregivers that potentially fatal additive effects may occur if methadone hydrochloride tablets are used with benzodiazepines or other CNS depressants (e.g., alcohol, non-benzodiazepine sedative/hypnotics, anxiolytics, tranquilizers, muscle relaxants, general anesthetics, antipsychotics, gabapentinoids [gabapentin or pregabalin], and other opioids), and not to use these concomitantly unless supervised by a health care provider [see WARNINGS AND PRECAUTIONS (5.3), DRUG INTERACTIONS (7)].

Patient Access to an Opioid Overdose Reversal Agent for the Emergency Treatment of Opioid Overdose

Inform patients and caregivers about opioid overdose reversal agents (e.g., naloxone, nalmefene) and discuss the importance of having access to an opioid reversal agent, both when initiating and renewing treatment with methadone hydrochloride tablets. Because patients being treated for opioid use disorder are at risk for relapse, discuss the importance of having access to an opioid overdose reversal agent. Also discuss the importance of having access to an opioid overdose reversal agent if the patient has household members (including children) or other close contacts at risk for accidental ingestion or opioid overdose.

Discuss with the patient the options for obtaining an opioid overdose reversal agent (e.g., prescription, over-the-counter (some products), or as part of a community-based program) [see DOSAGE AND ADMINISTRATION (2.3), WARNINGS AND PRECAUTIONS (5.2)].

There are important differences among the opioid overdose reversal agents. Be familiar with these differences, as outlined in the approved labeling for those products, prior to recommending or prescribing such an agent.

Educate patients and caregivers on how to recognize the signs and symptoms of an opioid overdose.

Explain to patients and caregivers that effects of opioid reversal agents like naloxone and nalmefene are temporary, and that they must call 911 or get emergency medical help right away in all cases of known or suspected opioid overdose, even if an opioid reversal agent is administered [see Overdosage (10)].

Advise patients and caregivers:

- how to treat with an opioid overdose reversal agent in the event of an opioid overdose
- to tell family and friends about their opioid overdose reversal agent, and to keep it in a place where family and friends can access it in an emergency
- to read the Patient Information (or other educational material) that will come with their opioid overdose reversal agent. Emphasize the importance of doing this before an opioid emergency happens, so the patient and caregiver will know what to do.

Hyperalgesia and Allodynia

Inform patients and caregivers not to increase opioid dosage without first consulting a clinician. Advise patients to seek medical attention if they experience symptoms of hyperalgesia, including worsening pain, increased sensitivity to pain, or new pain [see WARNINGS AND PRECAUTIONS (5.8); ADVERSE REACTIONS (6)].

Serotonin Syndrome

Inform patients that opioids could cause a rare but potentially life-threatening condition resulting from concomitant administration of serotonergic drugs. Warn patients of the symptoms of serotonin syndrome and to seek medical attention right away if symptoms develop. Instruct patients to inform their physicians if they are taking, or plan to take serotonergic medications [see WARNINGS AND PRECAUTIONS (5.9), DRUG INTERACTIONS (7)].

MAOI Interaction

Inform patients to avoid taking methadone hydrochloride tablets while using any drugs that inhibit monoamine oxidase. Patients should not start MAOIs while taking methadone hydrochloride tablets [see WARNINGS AND PRECAUTIONS (5.9), DRUG INTERACTIONS (7)].

Important Administration Instructions

Instruct patients how to properly take methadone hydrochloride tablets, including the following:

- Use methadone hydrochloride tablets exactly as prescribed to reduce the risk of life-threatening adverse reactions (e.g., respiratory depression) [see DOSAGE AND ADMINISTRATION (2), WARNINGS AND PRECAUTIONS (5.2)].

Important Discontinuation Instructions

In order to avoid developing withdrawal symptoms, instruct patients not to discontinue methadone hydrochloride tablets without first discussing a tapering plan with the prescriber [see DOSAGE AND ADMINISTRATION (2.6)].

Driving or Operating Heavy Machinery

Inform patients that methadone hydrochloride tablets may impair the ability to perform potentially hazardous activities such as driving a car or operating heavy machinery. Advise patients not to perform such tasks until they know how they will react to the medication [see WARNINGS AND PRECAUTIONS (5.17)].

Constipation

Advise patients of the potential for severe constipation, including management instructions and when to seek medical attention [see ADVERSE REACTIONS (6), CLINICAL PHARMACOLOGY (12.2).

Adrenal Insufficiency

Inform patients that opioids could cause adrenal insufficiency, a potentially life-threatening condition. Adrenal insufficiency may present with non-specific symptoms and signs such as nausea, vomiting, anorexia, fatigue, weakness, dizziness, and low blood pressure. Advise patients to seek medical attention if they experience a constellation of these symptoms [see WARNINGS AND PRECAUTIONS (5.11)].

Hypotension

Inform patients that methadone hydrochloride tablets may cause orthostatic hypotension and syncope. Instruct patients how to recognize symptoms of low blood pressure and how to reduce the risk of serious consequences should hypotension occur (e.g., sit or lie down, carefully rise from a sitting or lying position) [see WARNINGS AND PRECAUTIONS (5.12)].

Anaphylaxis

Inform patients that anaphylaxis has been reported with ingredients contained in methadone hydrochloride tablets. Advise patients how to recognize such a reaction and when to seek medical attention [see CONTRAINDICATIONS (4), ADVERSE REACTIONS (6)].

Pregnancy

Neonatal Opioid Withdrawal Syndrome: Inform female patients of reproductive potential that use of methadone hydrochloride tablets for an extended period of time during pregnancy can result in neonatal opioid withdrawal syndrome, which may be life-threatening if not recognized and treated [see WARNINGS AND PRECAUTIONS (5.5), SPECIFIC POPULATIONS (8.1)].

Embryo-Fetal Toxicity: Inform female patients of reproductive potential that methadone hydrochloride tablets can cause fetal harm and to inform their healthcare provider of a known or suspected pregnancy [see USE IN SPECIFIC POPULATIONS (8.1)].

Lactation

Advise women who are breastfeeding to carefully observe the infant for increased sleepiness (more than usual), difficulty breathing or limpness. Instruct nursing mothers using methadone hydrochloride tablets to watch for signs of methadone toxicity in their infants, which include increased sleepiness (more than usual), difficulty breastfeeding, breathing difficulties, or limpness. Instruct nursing mothers to talk to the baby’s healthcare provider immediately if they notice these signs. If they cannot reach the healthcare provider right away, instruct them to take the baby to the emergency room or call 911 (or local emergency services) [see USE IN SPECIFIC POPULATIONS (8.2)].

Infertility

Inform patients that use of opioids for an extended period of time may cause reduced fertility. It is not known whether these effects on fertility are reversible [see USE IN SPECIFIC POPULATIONS (8.3)].

Hypoglycemia

Inform patients that methadone may cause hypoglycemia. Instruct patients how to recognize the symptoms of low blood glucose and to contact their health care provider if these symptoms occur [see WARNINGS AND PRECAUTIONS (5.18)].

Distributed by:

VistaPharm, LLC
Parsippany, NJ 07054, USA

VP2002R5
12/2025

MEDICATION GUIDE

Methadone (METH-ah-done) Hydrochloride Tablets, USP, CII

Rx only

Methadone hydrochloride tablets are:

- A strong prescription pain medicine that contains an opioid (narcotic) that is used to manage severe and persistent pain that requires an extended treatment period with a daily opioid pain medicine when other pain medicines do not treat your pain well enough or you cannot tolerate them.
- A long-acting opioid pain medicine that can put you at risk for overdose and death. Even if you take your dose correctly as prescribed you are at risk for opioid addiction, abuse, and misuse than can lead to death.
- Not to be taken on an "as needed" basis.
- Also used to manage drug addiction.

Important information about methadone hydrochloride tablets:

- Get emergency help or call 911 right away if you take too much methadone hydrochloride tablets (overdose). When you first start taking methadone hydrochloride tablets, when your dose is changed, or if you take too much (overdose), serious or life-threatening breathing problems that can lead to death may occur. Ask your healthcare provider about medicines like naloxone or nalmefene that can be used in an emergency to reverse an opioid overdose, a medicine for the emergency treatment of an opioid overdose.
- Taking methadone hydrochloride tablets with other opioid medicines, benzodiazepines, gabapentinoids (gabapentin or pregabalin), alcohol, or other central nervous system depressants (including street drugs) can cause severe drowsiness, decreased awareness, breathing problems, coma, and death.
- Never give anyone else your methadone hydrochloride tablets. They could die from taking it. Selling or giving away methadone hydrochloride tablets is against the law.
- Store methadone hydrochloride tablets securely, out of sight and reach of children, and in a location not accessible by others, including visitors to the home.

Do not take methadone hydrochloride tablets if you have:

- Severe asthma, trouble breathing, or other lung problems.
- A bowel blockage or have narrowing of the stomach or intestines.

Before taking methadone hydrochloride tablets, tell your healthcare provider if you have a history of:

- head injury, seizures
- liver, kidney, thyroid problems
- problems urinating
- heart rhythm problems (Long QT syndrome)

- pancreas or gallbladder problems
- abuse of street or prescription drugs, alcohol addiction, opioid overdose, or mental health problems

Tell your healthcare provider if you are:

- Noticing your pain getting worse. If your pain gets worse after you take methadone hydrochloride tablets, do not take more of methadone hydrochloride tablets without first talking to your healthcare provider. Talk to your healthcare provider if the pain that you have increases, if you feel more sensitive to pain, or if you have new pain after taking methadone hydrochloride tablets.
- Pregnant or plan to become pregnant. If you take methadone hydrochloride tablets while pregnant, your baby may have symptoms of opioid withdrawal or respiratory depression at birth. Talk to your doctor if you are pregnant or plan to become pregnant.
- Breastfeeding. Methadone passes into breast milk and may harm your baby. Carefully observe infants for increased sleepiness (more than usual), breathing difficulties, or limpness. Seek immediate medical care if you notice these signs.
- Living in a household where there are small children or someone who has abused street or prescription drugs.
- Taking prescription or over-the-counter medicines, vitamins, or herbal supplements. Taking methadone hydrochloride tablets with certain other medicines may cause serious side effects.

When taking methadone hydrochloride tablets:

- Do not change your dose. Take methadone hydrochloride tablets exactly as prescribed by your healthcare provider. Use the lowest dose possible for the shortest time needed.
- Do not take more than your prescribed dose in 24 hours. If you take methadone hydrochloride tablets for pain and miss a dose, take methadone hydrochloride tablets as soon as possible and then take your next dose 8 or 12 hours later as directed by your healthcare provider. If it is almost time for your next dose, skip the missed dose and go back to your regular dosing schedule.
- If you take methadone hydrochloride tablets for opioid addiction and miss a dose, take your next dose the following day as scheduled. Do not take extra doses. Taking more than the prescribed dose may cause you to overdose because methadone hydrochloride tablets build up in your body over time.
- Do not crush, dissolve, snort or inject methadone hydrochloride tablets because this may cause you to overdose and die.
- Call your healthcare provider if the dose you are taking does not control your pain.
- Do not stop taking methadone hydrochloride tablets without talking to your healthcare provider.
- Dispose of expired, unwanted, or unused methadone hydrochloride tablets by taking your drug to an authorized DEA-registered collector or drug take-back program. If one is not available, you can dispose of methadone hydrochloride tablets by mixing the product with dirt, cat litter or coffee grounds; placing the mixture in a sealed bag, and throwing the bag in your trash. Visit www.fda.gov/drugdisposal for additional information on disposal of unused medicines.

While taking methadone hydrochloride tablets DO NOT:

- Drive or operate heavy machinery, until you know how methadone hydrochloride tablets affect you. Methadone hydrochloride tablets can make you sleepy, dizzy, or lightheaded.
- Drink alcohol or use prescription or over-the-counter medicines that contain alcohol. Using products containing alcohol during treatment with methadone hydrochloride tablets may cause you to overdose and die.

The possible side effects of methadone hydrochloride tablets are:

- Constipation, nausea, sleepiness, vomiting, tiredness, headache, dizziness, abdominal pain. Call your healthcare provider if you have any of these symptoms and they are severe.

Get emergency medical help or call 911 right away if you have:

- Trouble breathing, shortness of breath, fast heartbeat, chest pain, swelling of your face, tongue or throat, extreme drowsiness, light-headedness when changing positions, feeling faint, agitation, high body temperature, trouble walking, stiff muscles, or mental changes such as confusion.

These are not all the possible side effects of methadone hydrochloride tablets. Call your healthcare provider for medical advice about side effects. You may report side effects to FDA at 1-800-FDA-1088 or VistaPharm, LLC at 1-888-655-1505. For more information go to dailymed.nlm.nih.gov.

This Medication Guide has been approved by the U.S. Food and Drug Administration.

Distributed by:

VistaPharm, LLC
Parsippany, NJ 07054, USA

VP2113R5
12/2025

PRINCIPAL DISPLAY PANEL

NDC 66689-836-99

Methadone
Hydrochloride
Tablets, USP CII

10 mg

PHARMACIST: Dispense the accompanying
Medication Guide to each patient.

100 Tablets

Rx only

VistaPharm®
A PAI PHARMA COMPANY